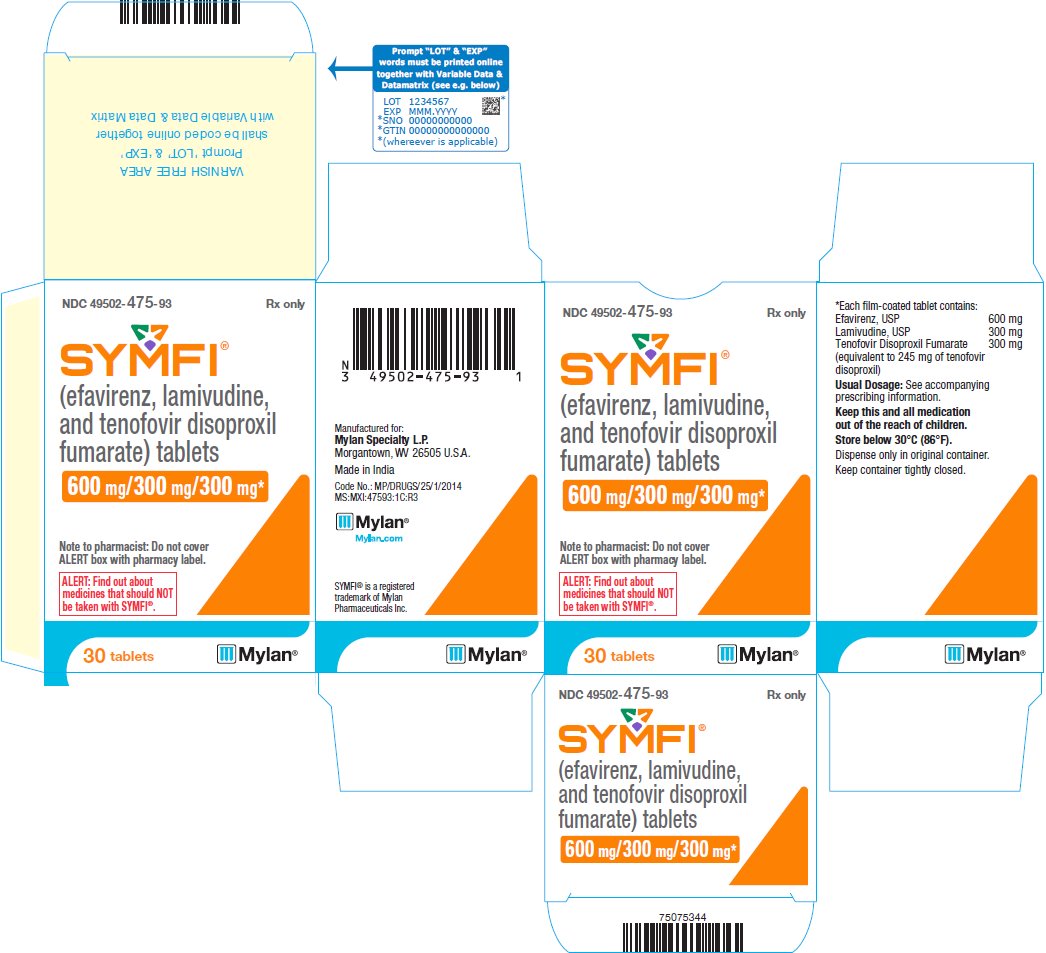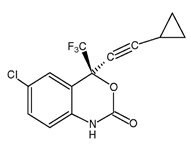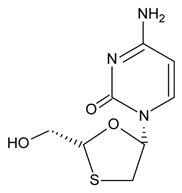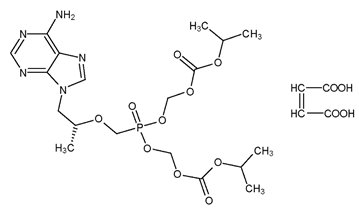 DRUG LABEL: SYMFI
NDC: 49502-475 | Form: TABLET, FILM COATED
Manufacturer: Viatris Specialty LLC
Category: prescription | Type: HUMAN PRESCRIPTION DRUG LABEL
Date: 20191015

ACTIVE INGREDIENTS: EFAVIRENZ 600 mg/1 1; LAMIVUDINE 300 mg/1 1; TENOFOVIR DISOPROXIL FUMARATE 300 mg/1 1
INACTIVE INGREDIENTS: CROSCARMELLOSE SODIUM; HYDROXYPROPYL CELLULOSE, UNSPECIFIED; LACTOSE MONOHYDRATE; MAGNESIUM STEARATE; MICROCRYSTALLINE CELLULOSE; POLYETHYLENE GLYCOL, UNSPECIFIED; POLYVINYL ALCOHOL, UNSPECIFIED; SODIUM CHLORIDE; SODIUM LAURYL SULFATE; TALC; TITANIUM DIOXIDE

HIGHLIGHTS OF PRESCRIBING INFORMATION

These highlights do not include all the information needed to use SYMFI safely and effectively. See full prescribing information for SYMFI.
SYMFI® (efavirenz, lamivudine and tenofovir disoproxil fumarate) tablets, for oral use
Initial U.S. Approval: 2018

RECENT MAJOR CHANGES

Warnings and Precautions (5.1, 5.2, 5.3, 5.4, 5.6, 5.13, 5.14) 10/2019

Warnings and Precautions, Use with Interferon- and Ribavirin-Based Regimens (previous 5.10) Removed 10/2019

WARNING: POST TREATMENT ACUTE EXACERBATIONS OF HEPATITIS B

See full prescribing information for complete boxed warning.

- Severe acute exacerbations of hepatitis B have been reported in patients who are co-infected with HBV and human immunodeficiency virus (HIV-1) and have discontinued lamivudine and tenofovir disoproxil fumarate. Monitor hepatic function closely in these patients and, if appropriate, initiate anti-hepatitis B treatment. (5.1)

1 INDICATIONS AND USAGE

SYMFI is a three-drug combination of efavirenz (EFV), a non-nucleoside reverse transcriptase inhibitor, and lamivudine (3TC) and tenofovir disoproxil fumarate (TDF), both nucleo(t)side reverse transcriptase inhibitors and is indicated as a complete regimen for the treatment of human immunodeficiency virus type 1 (HIV-1) infection in adult and pediatric patients weighing at least 40 kg. (1)

2 DOSAGE AND ADMINISTRATION

- Testing: Prior to initiation and during treatment with SYMFI, patients should be tested for hepatitis B virus infection, and estimated creatinine clearance, urine glucose, and urine protein should be obtained. (2.1)
- Recommended dose: One tablet taken orally once daily on an empty stomach, preferably at bedtime. (2.2)
- Renal Impairment: Not recommended in patients with CrCL less than 50 mL/min or patients with end-stage renal disease requiring hemodialysis. (2.3)
- Hepatic Impairment: Not recommended for patients with moderate or severe hepatic impairment. Use caution in patients with mild hepatic impairment. (2.4)

3 DOSAGE FORMS AND STRENGTHS

Tablets: 600 mg efavirenz, 300 mg lamivudine and 300 mg tenofovir disoproxil fumarate (equivalent to 245 mg of tenofovir disoproxil). (3)

4 CONTRAINDICATIONS

- SYMFI is contraindicated in patients with previous hypersensitivity (e.g., Stevens-Johnson syndrome, erythema multiforme, or toxic skin eruptions) to any of the components of this product. (4)
- Coadministration with elbasvir/grazoprevir. (4)

5 WARNINGS AND PRECAUTIONS

- Lactic Acidosis/Severe Hepatomegaly with Steatosis: Discontinue treatment in patients who develop symptoms or laboratory findings suggestive of lactic acidosis or pronounced hepatotoxicity. (5.2)
- New Onset or Worsening Renal Impairment: Can include acute renal failure and Fanconi syndrome. Avoid administering SYMFI with concurrent or recent use of nephrotoxic drugs. (5.4)
- Serious Psychiatric Symptoms:Immediate medical evaluation is recommended for serious psychiatric symptoms such as severe depression or suicidal ideation. (5.5)
- Nervous System Symptoms (NSS): NSS are frequent, usually begin 1 to 2 days after initiating therapy and resolve in 2 to 4 weeks. Dosing at bedtime may improve tolerability. NSS are not predictive of onset of psychiatric symptoms. (5.6)
- Rash: Rash usually begins within 1 to 2 weeks after initiating therapy and resolves within 4 weeks. Discontinue if severe rash develops. (5.8)
- Hepatotoxicity: Monitor liver function tests before and during treatment in patients with underlying hepatic disease, including hepatitis B or C coinfection, marked transaminase elevations, or who are taking medications associated with liver toxicity. Among reported cases of hepatic failure, a few occurred in patients with no pre-existing hepatic disease. (5.9, 8.7)
- Pancreatitis: Use with caution in pediatric patients with a history of pancreatitis or other significant risk factors for pancreatitis. Discontinue SYMFI as clinically appropriate. (5.10)
- Convulsions: Use caution in patients with a history of seizures. (5.11)
- Lipids: Total cholesterol and triglyceride elevations. Monitor before therapy and periodically thereafter. (5.12)
- Decreases in Bone Mineral Density (BMD): Observed in HIV-infected patients. Consider assessment of BMD in patients with a history of pathologic fracture or other risk factors for osteoporosis or bone loss. (5.13)
- Immune Reconstitution Syndrome: Observed in HIV-infected patients. May necessitate further evaluation and treatment. (5.14)
- Redistribution/Accumulation of Body Fat: Observed in HIV-infected patients receiving antiretroviral combination therapy. (5.15)

6 ADVERSE REACTIONS

- Most common adverse reactions are impaired concentration, abnormal dreams, headache, nausea, malaise and fatigue, nasal signs and symptoms, diarrhea, rash, dizziness, insomnia, pain, depression, asthenia, and cough. (6)

To report SUSPECTED ADVERSE REACTIONS, contact Mylan at 1-877-446-3679 (1-877-4-INFO-RX) or FDA at 1-800-FDA-1088 or www.fda.gov/medwatch.

7 DRUG INTERACTIONS

- SYMFI should not be administered with other antiretroviral medications for the treatment of HIV-1 infection. (7.1)
- Coadministration of SYMFI can alter the concentrations of other drugs and other drugs may alter the concentration of SYMFI. The potential for drug-drug interactions should be considered before and during therapy. (5.3, 7)

8 USE IN SPECIFIC POPULATIONS

- Pregnancy: Women should avoid pregnancy during EFV therapy, a component of SYMFI, and for 12 weeks after discontinuation. (5.7, 8.1, 8.3)
- Lactation: Breastfeeding not recommended due to potential for HIV transmission. (8.2)
- Females and Males of Reproductive Potential: Pregnancy testing and contraception are recommended. (8.3)

FULL PRESCRIBING INFORMATION

WARNING: POST TREATMENT ACUTE EXACERBATIONS OF HEPATITIS B

Severe acute exacerbations of hepatitis B have been reported in patients who are co-infected with hepatitis B virus (HBV) and human immunodeficiency virus (HIV-1) and have discontinued lamivudine or tenofovir disoproxil fumarate, two components of SYMFI. Monitor hepatic function closely in these patients and, if appropriate, initiate anti-hepatitis B treatment [see Warnings and Precautions (5.1)].

1 INDICATIONS AND USAGE

SYMFI® (efavirenz, lamivudine and tenofovir disoproxil fumarate) is indicated as a complete regimen for the treatment of human immunodeficiency virus type 1 (HIV-1) infection in adult and pediatric patients weighing at least 40 kg.

2 DOSAGE AND ADMINISTRATION

2.1 Testing Prior to Initiation and During Treatment with SYMFI

Prior to initiation of SYMFI, test patients for hepatitis B virus infection [see Warnings and Precautions (5.1)].

It is recommended that serum creatinine, serum phosphorus, estimated creatinine clearance, urine glucose, and urine protein be assessed before initiating SYMFI and during therapy in all patients as clinically appropriate [see Warnings and Precautions (5.4)].

Monitor hepatic function prior to and during treatment with SYMFI [see Warnings and Precautions (5.9)].

2.2 Recommended Dosage for Adult and Pediatric Patients Weighing at Least 40 kg

SYMFI is a three-drug fixed-dose combination product containing 600 mg of efavirenz (EFV), 300 mg of lamivudine (3TC), and 300 mg of tenofovir disoproxil fumarate (TDF). The recommended dosage of SYMFI in HIV-1-infected adults and pediatric patients who weigh at least 40 kg, and can swallow a solid tablet, is one tablet taken orally once daily. SYMFI tablets should be taken on an empty stomach, preferably at bedtime. Dosing at bedtime may improve the tolerability of nervous system symptoms [see Warnings and Precautions (5.6) and Adverse Reactions (6.1)].

2.3 Not Recommended in Renal Impairment

Because SYMFI is a fixed-dose combination tablet and cannot be dose adjusted, it is not recommended for patients with impaired renal function (creatinine clearance less than 50 mL/min) or patients with end-stage renal disease (ESRD) requiring hemodialysis [see Use in Specific Populations (8.6)].

2.4 Not Recommended in Moderate to Severe Hepatic Impairment

SYMFI is not recommended in patients with moderate or severe hepatic impairment (Child-Pugh B or C) [see Warnings and Precautions (5.9) and Use in Specific Populations (8.7)].

3 DOSAGE FORMS AND STRENGTHS

Tablets: 600 mg of efavirenz, 300 mg of lamivudine, and 300 mg of tenofovir disoproxil fumarate (equivalent to 245 mg of tenofovir disoproxil).

The tablets are white, film-coated, capsule shaped, debossed with M 152 on one side of the tablet and plain on the other side.

4 CONTRAINDICATIONS

SYMFI is contraindicated:

- in patients with a previous hypersensitivity reaction (e.g., Stevens-Johnson syndrome, erythema multiforme, or toxic skin eruptions) to any of the components contained in the formulation [see Warnings and Precautions (5.8)].
- when coadministered with elbasvir and grazoprevir [see Warnings and Precautions (5.3) and Drug Interactions (7.5)].

5 WARNINGS AND PRECAUTIONS

5.1 Severe Acute Exacerbation of Hepatitis B in Patients Coinfected with HIV-1 and HBV

Posttreatment Exacerbations of Hepatitis

All patients with HIV-1 should be tested for the presence of chronic hepatitis B virus (HBV) before initiating antiretroviral therapy [see Dosage and Administration (2.1)]. Discontinuation of anti-HBV therapy, including 3TC and TDF, may be associated with severe acute exacerbations of hepatitis B. Patients infected with HBV who discontinue SYMFI should be closely monitored with both clinical and laboratory follow-up for at least several months after stopping treatment. If appropriate, resumption of anti-hepatitis B therapy may be warranted.

Important Differences Among Lamivudine-Containing Products

SYMFI tablets contain a higher dose of the same active ingredient, 3TC, than EPIVIR-HBV® tablets. EPIVIR-HBV was developed for patients with chronic hepatitis B. The formulation and dosage of 3TC in EPIVIR-HBV are not appropriate for patients co-infected with HIV-1 and HBV. Safety and efficacy of 3TC have not been established for treatment of chronic hepatitis B in patients co-infected with HIV-1 and HBV.

If treatment with EPIVIR-HBV, TDF, or a tenofovir alafenamide (TAF)-containing product is prescribed for chronic hepatitis B for a patient with unrecognized or untreated HIV-1 infection, rapid emergence of HIV-1 resistance is likely to result because of the subtherapeutic dose and the inappropriateness of monotherapy HIV-1 treatment.

5.2 Lactic Acidosis and Severe Hepatomegaly with Steatosis

Lactic acidosis and severe hepatomegaly with steatosis, including fatal cases, have been reported with the use of nucleoside analogs and other antiretrovirals. Female sex and obesity may be risk factors for the development of lactic acidosis and severe hepatomegaly with steatosis in patients treated with antiretroviral nucleoside analogues. Treatment should be suspended in any patient who develops clinical or laboratory findings suggestive of lactic acidosis or pronounced hepatotoxicity, which may include hepatomegaly and steatosis even in the absence of marked transaminase elevations.

5.3 Risk of Adverse Reactions or Loss of Virologic Response Due to Drug Interactions

The concomitant use of SYMFI and other drugs may result in known or potentially significant drug interactions, some of which may lead to [see Contraindications (4) and Drug Interactions (7.5)]:

- Loss of therapeutic effect of SYMFI and possible development of resistance.
- Possible clinically significant adverse reactions from greater exposures of concomitant drugs.

See Table 3 for steps to prevent or manage these possible and known significant drug interactions, including dosing recommendations. Consider the potential for drug interactions prior to and during therapy with SYMFI; review concomitant medications during therapy with SYMFI; and monitor for the adverse reactions associated with the concomitant drugs.

5.4 New Onset or Worsening Renal Impairment

TDF, a component of SYMFI is principally eliminated by the kidney. Renal impairment, including cases of acute renal failure and Fanconi syndrome (renal tubular injury with severe hypophosphatemia), has been reported with the use of TDF [see Adverse Reactions (6.2)].

Prior to initiation and during use of SYMFI, on a clinically appropriate schedule, assess serum creatinine, estimated creatinine clearance, urine glucose, and urine protein in all patients.

Avoid SYMFI with concurrent or recent use of a nephrotoxic agent (e.g., high-dose or multiple non-steroidal anti-inflammatory drugs [NSAIDs]) [see Drug Interactions (7.3)]. Cases of acute renal failure after initiation of high-dose or multiple NSAIDs have been reported in HIV-infected patients with risk factors for renal dysfunction who appeared stable on TDF. Some patients required hospitalization and renal replacement therapy. Alternatives to NSAIDs should be considered, if needed, in patients at risk for renal dysfunction.

Persistent or worsening bone pain, pain in extremities, fractures and/or muscular pain or weakness may be manifestations of proximal renal tubulopathy and should prompt an evaluation of renal function in patients at risk of renal dysfunction.

5.5 Psychiatric Symptoms

Serious psychiatric adverse experiences have been reported in patients treated with EFV, a component of SYMFI. In controlled trials of 1008 patients treated with regimens containing EFV for a mean of 2.1 years and 635 patients treated with control regimens for a mean of 1.5 years, the frequency (regardless of causality) of specific serious psychiatric events among patients who received EFV or control regimens, respectively, were severe depression (2.4%, 0.9%), suicidal ideation (0.7%, 0.3%), nonfatal suicide attempts (0.5%, 0), aggressive behavior (0.4%, 0.5%), paranoid reactions (0.4%, 0.3%), and manic reactions (0.2%, 0.3%). When psychiatric symptoms similar to those noted above were combined and evaluated as a group in a multifactorial analysis of data from a study using EFV 600 mg, treatment with EFV was associated with an increase in the occurrence of these selected psychiatric symptoms. Other factors associated with an increase in the occurrence of these psychiatric symptoms were history of injection drug use, psychiatric history, and receipt of psychiatric medication at study entry; similar associations were observed in both the EFV and control treatment groups. In a study using EFV 600 mg, onset of new serious psychiatric symptoms occurred throughout the study for both EFV-treated and control-treated patients. One percent of EFV-treated patients discontinued or interrupted treatment because of one or more of these selected psychiatric symptoms.

There have also been occasional postmarketing reports of death by suicide, delusions, psychosis-like behavior, although a causal relationship to the use of EFV cannot be determined from these reports [see Adverse Reactions (6.2)]. Postmarketing cases of catatonia have also been reported and may be associated with increased efavirenz exposure. Patients with serious psychiatric adverse experiences should seek immediate medical evaluation to assess the possibility that the symptoms may be related to the use of EFV, and if so, to determine whether the risks of continued therapy outweigh the benefits.

5.6 Nervous System Symptoms

Fifty-three percent (531/1008) of patients receiving EFV, a component of SYMFI, in controlled trials reported central nervous system symptoms (any grade, regardless of causality) compared to 25% (156/635) of patients receiving control regimens. These symptoms included, but were not limited to, dizziness (28.1% of the 1008 patients), insomnia (16.3%), impaired concentration (8.3%), somnolence (7.0%), abnormal dreams (6.2%), and hallucinations (1.2%). These symptoms were severe in 2.0% of patients and 2.1% of patients discontinued therapy as a result. These symptoms usually begin during the first or second day of therapy and generally resolve after the first 2 to 4 weeks of therapy. After 4 weeks of therapy, the prevalence of nervous system symptoms of at least moderate severity ranged from 5% to 9% in patients treated with regimens containing EFV and from 3% to 5% in patients treated with a control regimen. Inform patients that these common symptoms were likely to improve with continued therapy and were not predictive of subsequent onset of the less frequent psychiatric symptoms [see Warnings and Precautions (5.5)]. Dosing at bedtime may improve the tolerability of these nervous system symptoms [see Dosage and Administration (2.2)].

Late-onset neurotoxicity, including ataxia and encephalopathy (impaired consciousness, confusion, psychomotor slowing, psychosis, delirium), may occur months to years after beginning efavirenz therapy. Some events of late-onset neurotoxicity have occurred in patients with CYP2B6 genetic polymorphisms which are associated with increased efavirenz levels despite daily dosages of 600 mg of efavirenz. Patients presenting with signs and symptoms of serious neurologic adverse experiences should be evaluated promptly to assess the possibility that these events may be related to efavirenz use, and whether discontinuation of SYMFI is warranted.

5.7 Embryo-Fetal Toxicity

EFV, a component of SYMFI, may cause fetal harm when administered during the first trimester to a pregnant woman. Advise females of reproductive potential who are receiving EFV to avoid pregnancy [see Use in Specific Populations (8.1, 8.3)].

5.8 Skin and Systemic Hypersensitivity Reaction

In controlled clinical trials, 26% (266/1008) of patients treated with 600 mg EFV experienced new-onset skin rash compared with 17% (111/635) of patients treated in control groups. Rash associated with blistering, moist desquamation, or ulceration occurred in 0.9% (9/1008) of patients treated with EFV. The incidence of Grade 4 rash (e.g., erythema multiforme, Stevens-Johnson syndrome) in patients treated with EFV in all studies and expanded access was 0.1%. Rashes are usually mild-to-moderate maculopapular skin eruptions that occur within the first 2 weeks of initiating therapy with EFV (median time to onset of rash in adults was 11 days) and, in most patients continuing therapy with EFV, rash resolves within 1 month (median duration, 16 days). The discontinuation rate for rash in clinical trials was 1.7% (17/1008).

EFV can generally be reinitiated in patients interrupting therapy because of rash. EFV should be discontinued in patients developing severe rash associated with blistering, desquamation, mucosal involvement, or fever. Appropriate antihistamines and/or corticosteroids may improve the tolerability and hasten the resolution of rash. For patients who have had a life-threatening cutaneous reaction (e.g., Stevens-Johnson syndrome), alternate therapy should be considered [see Contraindications (4)].

5.9 Hepatotoxicity

Postmarketing cases of hepatitis, including fulminant hepatitis progressing to liver failure requiring transplantation or resulting in death, have been reported in patients treated with EFV. Reports have included patients with underlying hepatic disease, including coinfection with hepatitis B or C, and patients without pre-existing hepatic disease or other identifiable risk factors.

EFV, a component of SYMFI, is not recommended for patients with moderate or severe hepatic impairment. Careful monitoring is recommended for patients with mild hepatic impairment receiving EFV [see Adverse Reactions (6.1) and Use in Specific Populations (8.7)].

Monitoring of liver enzymes before and during treatment is recommended for all patients [see Dosage and Administration (2.1)]. Consider discontinuing SYMFI in patients with persistent elevations of serum transaminases to greater than five times the upper limit of the normal range.

Discontinue SYMFI if elevation of serum transaminases is accompanied by clinical signs or symptoms of hepatitis or hepatic decompensation.

5.10 Pancreatitis

In pediatric patients with a history of prior antiretroviral nucleoside exposure, a history of pancreatitis, or other significant risk factors for the development of pancreatitis, 3TC, a component of SYMFI, should be used with caution. Treatment with SYMFI should be stopped immediately if clinical signs, symptoms, or laboratory abnormalities suggestive of pancreatitis occur [see Adverse Reactions (6.1)].

5.11 Convulsions

Convulsions have been observed in patients receiving EFV, generally in the presence of known medical history of seizures [see Nonclinical Toxicology (13.2)]. Caution should be taken in any patient with a history of seizures. Patients who are receiving concomitant anticonvulsant medications primarily metabolized by the liver, such as phenytoin and phenobarbital, may require periodic monitoring of plasma levels [see Drug Interactions (7.5)].

5.12 Lipid Elevations

Treatment with EFV has resulted in increases in the concentration of total cholesterol and triglycerides. Cholesterol and triglyceride testing should be performed before initiating EFV therapy and at periodic intervals during therapy.

5.13 Bone Loss and Mineralization Effects

Bone Mineral Density (BMD)

In clinical trials in HIV-1-infected adults, TDF was associated with slightly greater decreases in BMD and increases in biochemical markers of bone metabolism, suggesting increased bone turnover relative to comparators [see Adverse Reactions (6.1)]. Serum parathyroid hormone levels and 1,25 Vitamin D levels were also higher in subjects receiving TDF.

The effects of TDF-associated changes in BMD and biochemical markers on long-term bone health and future fracture risk in adults and pediatric subjects 2 years and older are unknown. The long-term effect of lower spine and total body BMD on skeletal growth in pediatric patients, and in particular, the effects of long-duration exposuire in younger children is unknown.

Although the effect of supplementation with calcium and vitamin D was not studied, such supplementation may be beneficial. Assessment of BMD should be considered for adult and pediatric patients who have a history of pathologic bone fracture or other risk factors for osteoporosis or bone loss. If bone abnormalities are suspected then appropriate consultation should be obtained.

Mineralization Defects

Cases of osteomalacia associated with proximal renal tubulopathy, manifested as bone pain or pain in extremities and which may contribute to fractures, have been reported in association with TDF use [see Adverse Reactions (6.2)]. Arthralgia and muscle pain or weakness have also been reported in cases of proximal renal tubulopathy. Hypophosphatemia and osteomalacia secondary to proximal renal tubulopathy should be considered in patients at risk of renal dysfunction who present with persistent or worsening bone or muscle symptoms while receiving TDF-containing products [see Warnings and Precautions (5.4)].

5.14 Immune Reconstitution Syndrome

Immune reconstitution syndrome has been reported in HIV-infected patients treated with combination antiretroviral therapy, including EFV, 3TC, and TDF. During the initial phase of combination antiretroviral treatment, patients whose immune system responds may develop an inflammatory response to indolent or residual opportunistic infections (such as Mycobacterium avium infection, cytomegalovirus, Pneumocystis jirovecii pneumonia [PCP], or tuberculosis), which may necessitate further evaluation and treatment.

Autoimmune disorders (such as Graves’ disease, polymyositis, Guillain-Barre syndrome, and autoimmune hepatitis) have also been reported to occur in the setting of immune reconstitution; however, the time to onset is more variable, and can occur many months after initiation of treatment.

5.15 Fat Redistribution

In HIV-infected patients, redistribution/accumulation of body fat including central obesity, dorsocervical fat enlargement (buffalo hump), peripheral wasting, facial wasting, breast enlargement, and “cushingoid appearance” have been observed in patients receiving combination antiretroviral therapy. The mechanism and long-term consequences of these events are currently unknown. A causal relationship has not been established.

5.16 QTc Prolongation

QTc prolongation has been observed with the use of EFV [see Drug Interactions (7.2, 7.5) and Clinical Pharmacology (12.2)]. Consider alternatives to products containing EFV when coadministered with a drug with a known risk of Torsade de Pointes or when administered to patients at higher risk of Torsade de Pointes.

6 ADVERSE REACTIONS

The following adverse reactions are discussed in other sections of the labeling:

- Exacerbations of Hepatitis B [see Boxed Warning, Warnings and Precautions (5.1)].
- Lactic Acidosis/Severe Hepatomegaly with Steatosis [see Warnings and Precautions (5.2)].
- New Onset or Worsening Renal Impairment [see Warnings and Precautions (5.4)].
- Psychiatric Symptoms [see Warnings and Precautions (5.5)].
- Nervous System Symptoms [see Warnings and Precautions (5.6)].
- Skin and Systemic Hypersensitivity Reaction [see Warnings and Precautions (5.8)].
- Hepatotoxicity [see Warnings and Precautions (5.9)].
- Pancreatitis [see Warnings and Precautions (5.10)].
- Bone Loss and Mineralization Effects [see Warnings and Precautions (5.13)].
- Immune Reconstitution Syndrome [see Warnings and Precautions (5.14)].
- Fat Redistribution [see Warnings and Precautions (5.15)].

6.1 Clinical Trials Experience

Because clinical studies are conducted under widely varying conditions, the adverse reaction rates observed in clinical trials of a drug cannot be directly compared to rates in the clinical trials of another drug and may not reflect the rates observed in practice.

Efavirenz, Lamivudine and Tenofovir Disoproxil Fumarate

Clinical Trials in Treatment-Naïve HIV-1 Infected Adult Subjects

In Trial 903, 600 antiretroviral-naïve subjects received TDF (N = 299) or stavudine (d4T) (N = 301) administered in combination with 3TC and EFV for 144 weeks. The most common adverse reactions were mild to moderate gastrointestinal events and dizziness. Mild adverse reactions (Grade 1) were common with a similar incidence in both arms and included dizziness, diarrhea, and nausea. Table 1 provides the treatment-emergent adverse reactions (Grades 2-4) occurring in greater than or equal to 5% of subjects treated in any treatment group.

Table 1. Selected Adverse Reactions [Frequencies of adverse reactions are based on all treatment-emergent adverse events, regardless of relationship to study drug.] (Grades 2-4) Reported in ≥ 5% in Any Treatment Group in Trial 903 (0-144 Weeks)
 | TDF + 3TC + EFV | d4T + 3TC + EFV
 | N = 299 | N = 301
Rash event [Rash event includes rash, pruritus, maculopapular rash, urticaria, vesiculobullous rash, and pustular rash.] | 18% | 12%
Headache | 14% | 17%
Pain | 13% | 12%
Diarrhea | 11% | 13%
Depression | 11% | 10%
Back pain | 9% | 8%
Nausea | 8% | 9%
Fever | 8% | 7%
Abdominal pain | 7% | 12%
Asthenia | 6% | 7%
Anxiety | 6% | 6%
Vomiting | 5% | 9%
Insomnia | 5% | 8%
Arthralgia | 5% | 7%
Pneumonia | 5% | 5%
Dyspepsia | 4% | 5%
Dizziness | 3% | 6%
Myalgia | 3% | 5%
Lipodystrophy [Lipodystrophy represents a variety of investigator-described adverse events not a protocol-defined syndrome.] | 1% | 8%
Peripheral neuropathy [Peripheral neuropathy includes peripheral neuritis and neuropathy.] | 1% | 5%

Laboratory Abnormalities

Table 2 provides a list of laboratory abnormalities (Grades 3-4) observed in Trial 903. With the exception of fasting cholesterol and fasting triglyceride elevations that were more common in the d4T group (40% and 9%) compared with the TDF group (19% and 1%) respectively, laboratory abnormalities observed in this trial occurred with similar frequency in the TDF and d4T treatment arms.

Table 2. Grade 3-4 Laboratory Abnormalities Reported in ≥ 1% of Patients Randomized to Efavirenz, Lamivudine and Tenofovir Disoproxil Fumarate in Study 903 (0-144 Weeks)
 | TDF + 3TC + EFV | d4T + 3TC + EFV
 | N = 299 | N = 301
Any ≥ Grade 3 Laboratory Abnormality | 36% | 42%
Fasting Cholesterol (> 240 mg/dL) | 19% | 40%
Creatine Kinase (M: > 990 U/L; F: > 845 U/L) | 12% | 12%
Serum Amylase (> 175 U/L) | 9% | 8%
AST (M: > 180 U/L; F: > 170 U/L) | 5% | 7%
ALT (M: > 215 U/L; F: > 170 U/L) | 4% | 5%
Hematuria (> 100 RBC/HPF) | 7% | 7%
Neutrophils (< 750/mm^3) | 3% | 1%
Fasting Triglycerides (> 750 mg/dL) | 1% | 9%

Pancreatitis

Pancreatitis, which has been fatal in some cases, has been observed in antiretroviral nucleoside-experienced pediatric subjects receiving 3TC alone or in combination with other antiretroviral agents [see Warnings and Precautions (5.10)].

Changes in Bone Mineral Density

In HIV-1-infected adult subjects in Trial 903, there was a significantly greater mean percentage decrease from baseline in BMD at the lumbar spine in subjects receiving TDF + 3TC + EFV (-2.2% ± 3.9) compared with subjects receiving d4T + 3TC + EFV (-1.0% ± 4.6) through 144 weeks. Changes in BMD at the hip were similar between the two treatment groups (-2.8% ± 3.5 in the TDF group vs. -2.4% ± 4.5 in the d4T group). In both groups, the majority of the reduction in BMD occurred in the first 24-48 weeks of the trial and this reduction was sustained through Week 144. Twenty-eight percent of TDF-treated subjects vs. 21% of the d4T-treated subjects lost at least 5% of BMD at the spine or 7% of BMD at the hip. Clinically relevant fractures (excluding fingers and toes) were reported in 4 subjects in the TDF group and 6 subjects in the d4T group. In addition, there were significant increases in biochemical markers of bone metabolism (serum bone-specific alkaline phosphatase, serum osteocalcin, serum C telopeptide, and urinary N telopeptide) and higher serum parathyroid hormone levels and 1,25 Vitamin D levels in the TDF group relative to the d4T group; however, except for bone-specific alkaline phosphatase, these changes resulted in values that remained within the normal range [see Warnings and Precautions (5.13)].

6.2 Postmarketing Experience

The following adverse reactions have been identified during post-approval use for each of the individual components of SYMFI (EFV, 3TC, and TDF). Because these reactions are reported voluntarily from a population of unknown size, it is not always possible to reliably estimate their frequency or establish causal relationship to drug exposure. These reactions have been chosen for inclusion due to a combination of their seriousness, frequency of reporting, or potential causal connection to EFV, 3TC, and TDF.

Efavirenz

Body as a Whole: allergic reactions, asthenia, redistribution/accumulation of body fat [see Warnings and Precautions (5.15)].

Central and Peripheral Nervous System: abnormal coordination, ataxia, encephalopathy, cerebellar coordination and balance disturbances, convulsions, hypoesthesia, paresthesia, neuropathy, tremor, vertigo.

Endocrine: gynecomastia.

Gastrointestinal: constipation, malabsorption.

Cardiovascular: flushing, palpitations.

Liver and Biliary System: hepatic enzyme increase, hepatic failure, hepatitis.

Metabolic and Nutritional: hypercholesterolemia, hypertriglyceridemia.

Musculoskeletal: arthralgia, myalgia, myopathy.

Psychiatric: aggressive reactions, agitation, delusions, emotional lability, mania, neurosis, paranoia, psychosis, suicide, catatonia.

Respiratory: dyspnea.

Skin and Appendages: erythema multiforme, photoallergic dermatitis, Stevens-Johnson syndrome.

Special Senses: abnormal vision, tinnitus.

Lamivudine

Body as a Whole: redistribution/accumulation of body fat [see Warnings and Precautions (5.15)].

Endocrine and Metabolic: hyperglycemia.

General: weakness.

Hemic and Lymphatic: anemia (including pure red cell aplasia and severe anemias progressing on therapy).

Hepatic and Pancreatic: lactic acidosis and hepatic steatosis, posttreatment exacerbation of hepatitis B [see Boxed Warning, Warnings and Precautions (5.1, 5.2)].

Hypersensitivity: anaphylaxis, urticaria.

Musculoskeletal: muscle weakness, CPK elevation, rhabdomyolysis.

Skin: Alopecia, pruritus.

Tenofovir Disoproxil Fumarate

Immune System Disorders: allergic reaction, including angioedema.

Metabolism and Nutrition Disorders: lactic acidosis, hypokalemia, hypophosphatemia.

Respiratory, Thoracic, and Mediastinal Disorders: dyspnea.

Gastrointestinal Disorders: pancreatitis, increased amylase, abdominal pain.

Renal and Urinary Disorders: renal insufficiency, acute renal failure, renal failure, acute tubular necrosis, Fanconi syndrome, proximal renal tubulopathy, interstitial nephritis (including acute cases), nephrogenic diabetes insipidus, renal insufficiency, increased creatinine, proteinuria, polyuria [see Warnings and Precautions (5.4)].

Hepatobiliary Disorders: hepatic steatosis, hepatitis, increased liver enzymes (most commonly AST, ALT gamma GT).

Skin and Subcutaneous Tissue Disorders: rash.

Musculoskeletal and Connective Tissue Disorders: rhabdomyolysis, osteomalacia (manifested as bone pain and which may contribute to fractures), muscular weakness, myopathy.

General Disorders and Administration Site Conditions: asthenia.

The following adverse reactions, listed under the body system headings above, may occur as a consequence of proximal renal tubulopathy: rhabdomyolysis, osteomalacia, hypokalemia, muscular weakness, myopathy, hypophosphatemia.

7 DRUG INTERACTIONS

7.1 Not Recommended with Other Antiretroviral Medications

SYMFI is a complete regimen for the treatment of HIV-1 infection; therefore, it should not be administered with other antiretroviral medications for treatment of HIV-1 infection.

7.2 QT Prolonging Drugs

There is limited information available on the potential for a pharmacodynamic interaction between EFV and drugs that prolong the QTc interval. QTc prolongation has been observed with the use of EFV [see Clinical Pharmacology (12.2)]. Consider alternatives to EFV when coadministered with a drug with a known risk of Torsade de Pointes.

7.3 Drugs Affecting Renal Function

Tenofovir is primarily eliminated by the kidneys [see Clinical Pharmacology (12.3)]. Coadministration of EFV/3TC/TDF with drugs that are eliminated by active tubular secretion may increase concentrations of tenofovir and/or the coadministered drug. Some examples include, but are not limited to, acyclovir, cidofovir, ganciclovir, valacyclovir, valganciclovir, aminoglycosides (e.g., gentamicin), and high-dose or multiple NSAIDs [see Warnings and Precautions (5.4)]. Drugs that decrease renal function may increase concentrations of tenofovir.

7.4 Cannabinoid Test Interaction

EFV does not bind to cannabinoid receptors. False-positive urine cannabinoid test results have been reported with some screening assays in uninfected and HIV-infected subjects receiving EFV. Confirmation of positive screening tests for cannabinoids by a more specific method is recommended.

7.5 Established and Other Potentially Significant Interactions

EFV has been shown in vivo to induce CYP3A and CYP2B6. Other compounds that are substrates of CYP3A or CYP2B6 may have decreased plasma concentrations when coadministered with EFV.

Drugs that induce CYP3A activity (e.g., phenobarbital, rifampin, rifabutin) would be expected to increase the clearance of EFV resulting in lowered plasma concentrations.

No drug interaction studies have been conducted using SYMFI. However, drug interaction studies have been conducted with the individual components of SYMFI (EFV, 3TC, and TDF) [see Clinical Pharmacology (12.3)].

Drug interactions with EFV are summarized in Table 3 [for pharmacokinetics data see Clinical Pharmacology (12.3, Tables 6 and 7)]. This table includes potentially significant interactions, but is not all inclusive.

Table 3. Established and Other Potentially Significant Drug Interactions with EFV: Alteration in Dose or Regimen May Be Recommended Based on Drug Interaction Studies or Predicted Interaction
Concomitant Drug; Class: Drug Name | Effect | Clinical Comment
Anticoagulant:; Warfarin | ↑ or ↓ warfarin | Monitor INR and adjust warfarin dosage if necessary.
Anticonvulsants:; Carbamazepine | ↓ carbamazepine [The interaction between EFV and the drug was evaluated in a clinical study. All other drug interactions shown are predicted.]; ↓ EFV* | There are insufficient data to make a dose recommendation for EFV. Alternative anticonvulsant treatment should be used.
Phenytoin; Phenobarbital | ↓ anticonvulsant; ↓ EFV | Monitor anticonvulsant plasma levels periodically because of potential for reduction in anticonvulsant and/or EFV plasma levels.
Antidepressants:; Bupropion | ↓ bupropion | Increases in bupropion dosage should be guided by clinical response. Bupropion dose should not exceed the maximum recommended dose.
Sertraline | ↓ sertraline | Increases in sertraline dosage should be guided by clinical response.
Antifungals:; Itraconazole; Ketoconazole | ↓ itraconazole; ↓ hydroxyitraconazole; ↓ ketoconazole | Consider alternative antifungal treatment because no dose recommendation for itraconazole or ketoconazole can be made.
Posaconazole | ↓ posaconazole | Avoid concomitant use unless the benefit outweighs the risks.
Anti-infective:; Clarithromycin | ↓ clarithromycin; ↑ 14-OH metabolite | Consider alternatives to macrolide antibiotics because of the risk of QT interval prolongation.
Antimycobacterial:; Rifabutin | ↓ rifabutin | Increase daily dose of rifabutin by 50%. Consider doubling the rifabutin dose in regimens where rifabutin is given 2 or 3 times a week.
Rifampin | ↓ EFV | Increase EFV total daily dose to 800 mg once daily when coadministered with rifampin to patients weighing 50 kg or more.
Antimalarials:; Artemether/lumefantrine | ↓ artemether; ↓ dihydroartemisinin; ↓ lumefantrine | Consider alternatives to artemether/lumefantrine because of the risk of QT interval prolongation [see Warnings and Precautions (5.16)].
Atovaquone/; proguanil | ↓ atovaquone; ↓ proguanil | Concomitant administration is not recommended.
Calcium channel blockers:; Diltiazem | ↓ diltiazem; ↓ desacetyl diltiazem; ↓ N-monodesmethyldiltiazem | Diltiazem dose adjustments should be guided by clinical response (refer to the full prescribing information for diltiazem).
Others (e.g., felodipine,; nicardipine, nifedipine,; verapamil) | ↓ calcium channel blocker | When coadministered with EFV, dosage adjustment of calcium channel blocker may be needed and should be guided by clinical response (refer to the full prescribing information for the calcium channel blocker).
HMG-CoA reductase inhibitors:; Atorvastatin; Pravastatin; Simvastatin | ↓ atorvastatin; ↓ pravastatin; ↓ simvastatin | Plasma concentrations of atorvastatin, pravastatin, and simvastatin decreased. Consult the full prescribing information for the HMG-CoA reductase inhibitor for guidance on individualizing the dose.
Hepatitis C antiviral agents:; Boceprevir | ↓ boceprevir | Concomitant administration of boceprevir is not recommended.
Elbasvir/Grazoprevir | ↓ elbasvir; ↓ grazoprevir | Coadministration of EFV with elbasvir/grazoprevir is contraindicated [see Contraindications (4)] because it may lead to loss of virologic response to elbasvir/grazoprevir.
Pibrentasvir/Glecaprevir | ↓ pibrentasvir; ↓ glecaprevir | Coadministration of EFV is not recommended because it may lead to reduced therapeutic effect of pibrentasvir/glecaprevir.
Simeprevir | ↓ simeprevir; ↔ EFV | Concomitant administration of simeprevir is not recommended.
Velpatasvir/Sofosbuvir | ↓ velpatasvir | Coadministration of EFV and sofosbuvir/velpatasvir is not recommended because it may result in loss of therapeutic effect of sofosbuvir/velpatasvir.
Velpatasvir/Sofosbuvir/ Voxilaprevir | ↓ velpatasvir; ↓ voxilaprevir | Coadministration of EFV and sofosbuvir/velpatasvir/voxilaprevir is not recommended because it may result in loss of therapeutic effect of sofosbuvir/velpatasvir/voxilaprevir.
Ledipasvir/Sofosbuvir | ↑ TDF | Monitor for adverse reactions associated with TDF.
Hepatitis B antiviral agents; Adefovir dipivoxil |  | Concomitant administration of adefovir dipivoxil is not recommended.
Hormonal contraceptives:; Oral Ethinyl estradiol/ Norgestimate | ↓ active metabolites of norgestimate | A reliable method of barrier contraception should be used in addition to hormonal contraceptives.
Implant Etonogestrel | ↓ etonogestrel | A reliable method of barrier contraception should be used in addition to hormonal contraceptives. Decreased exposure of etonogestrel may be expected. There have been postmarketing reports of contraceptive failure with etonogestrel in EFV-exposed patients.
Immunosuppressants: Cyclosporine, tacrolimus,; sirolimus, and others metabolized by CYP3A | ↓ immunosuppressant | Dose adjustments of the immunosuppressant may be required. Close monitoring of immunosuppressant concentrations for at least 2 weeks (until stable concentrations are reached) is recommended when starting or stopping treatment with EFV.
Narcotic analgesic:; Methadone | ↓ methadone | Monitor for signs of methadone withdrawal and increase methadone dose if required to alleviate withdrawal symptoms.
This table is not all-inclusive.

7.6 Drugs without Clinically Significant Interactions

No dosage adjustment is recommended when SYMFI is administered with the following: aluminum/magnesium hydroxide antacids, azithromycin, cetirizine, famotidine, fluconazole, and lorazepam.

7.7 Drugs Inhibiting Organic Cation Transporters

3TC, a component of SYMFI, is predominantly eliminated in the urine by active organic cationic secretion. The possibility of interactions with other drugs administered concurrently should be considered, particularly when their main route of elimination is active renal secretion via the organic cationic transport system (e.g., trimethoprim) [see Clinical Pharmacology (12.3)]. No data are available regarding interactions with other drugs that have renal clearance mechanisms similar to that of 3TC.

7.8 Sorbitol

Coadministration of single doses of 3TC and sorbitol resulted in a sorbitol dose-dependent reduction in 3TC exposures. When possible, avoid use of sorbitol-containing medicines with 3TC [see Clinical Pharmacology (12.3)].

8 USE IN SPECIFIC POPULATIONS

8.1 Pregnancy

Pregnancy Exposure Registry

There is a pregnancy exposure registry that monitors pregnancy outcomes in women exposed to SYMFI during pregnancy. Healthcare providers are encouraged to register patients by calling the Antiretroviral Pregnancy Registry (APR) at 1-800-258-4263.

Risk Summary

There are retrospective case reports of neural tube defects in infants whose mothers were exposed to EFV-containing regimens in the first trimester of pregnancy.

Although a causal relationship has not been established between exposure to EFV in the first trimester and neural tube defects, similar malformations have been observed in studies conducted in monkeys at doses similar to the human dose. In addition, fetal and embryonic toxicities occurred in rats, at a dose ten times less than the human exposure at recommended clinical dose. Because of the potential risk of neural tube defects, EFV should not be used in the first trimester of pregnancy. Advise pregnant women of the potential risk to a fetus.

Prospective pregnancy data from the APR are not sufficient to adequately assess this risk of birth defects or miscarriage. EFV and 3TC have been evaluated in a limited number of women as reported to the APR. Available data from the APR show no difference in the risk of major birth defects for EFV and 3TC compared to the background rate for major birth defects of 2.7% in the U.S. reference population of the Metropolitan Atlanta Congenital Defects Program (MACDP).

Available data from the APR also show no increase in the overall risk of major birth defects with first trimester exposure for TDF (2.1%) compared with the background rate for major birth defects of 2.7% in a U.S. reference population of the MACDP (see Data).

3TC produced embryonic toxicity in rabbits at a dose that produced similar human exposures as the recommended clinical dose. The relevance of animal findings to human pregnancy registry data is not known.

The rate of miscarriage is not reported in the APR. The estimated background rate of miscarriage in clinically recognized pregnancies in the U.S. general population is 15% to 20%. The background risk for major birth defects and miscarriage for the indicated population is unknown. The APR uses the MACDP as the U.S. reference population for birth defects in the general population. The MACDP evaluates women and infants from a limited geographic area and does not include outcomes for births that occurred at less than 20 weeks’ gestation.

Human Data

Efavirenz

There are retrospective postmarketing reports of findings consistent with neural tube defects, including meningomyelocele, all in infants of mothers exposed to EFV-containing regimens in the first trimester [see Warnings and Precautions (5.7)].

Based on prospective reports from the APR of approximately 1000 live births following exposure to EFV-containing regimens (including over 800 live births exposed in the first trimester), there was no difference between EFV and overall birth defects compared with the background birth defect rate of 2.7% in the U.S. reference population of the Metropolitan Atlanta Congenital Defects Program. As of the interim APR report issued December 2014, the prevalence of birth defects following first-trimester exposure was 2.3% (95% CI: 1.4%-3.6%). One of these prospectively reported defects with first-trimester exposure was a neural tube defect. A single case of anophthalmia with first-trimester exposure to EFV has also been prospectively reported. This case also included severe oblique facial clefts and amniotic banding, which have a known association with anophthalmia.

Lamivudine

Based on prospective reports from the APR of over 11,000 exposures to 3TC during pregnancy resulting in live births (including over 4,300 exposed in the first trimester), there was no difference between 3TC and overall risk of birth defects for 3TC compared with the background birth defect rate of 2.7% in the U.S. reference population of the MACDP. The prevalence of defects in live births was 3.1% (95% CI: 2.6% to 3.6%) following first trimester exposure to 3TC-containing regimens and 2.8% (95% CI: 2.5% to 3.3%) following second/third trimester exposure to 3TC-containing regimens.

3TC pharmacokinetics were studied in pregnant women during 2 clinical trials conducted in South Africa. The trials assessed pharmacokinetics in 16 women at 36 weeks’ gestation using 150 mg 3TC twice daily with zidovudine, 10 women at 38 weeks’ gestation using 150 mg 3TC twice daily with zidovudine, and 10 women at 38 weeks’ gestation using 3TC 300 mg twice daily without other antiretrovirals. These trials were not designed or powered to provide efficacy information.

3TC concentrations were generally similar in maternal, neonatal, and umbilical cord serum samples. In a subset of subjects, amniotic fluid specimens were collected following natural rupture of membranes and confirmed that 3TC crosses the placenta in humans. Based on limited data at delivery, median (range) amniotic fluid concentrations of 3TC were 3.9 (1.2 to 12.8)-fold greater compared with paired maternal serum concentration (n = 8).

Tenofovir Disoproxil Fumarate

Based on prospective reports from the APR exposures to TDF-containing regimens during pregnancy resulting in live births (including 3,342 exposed in the first trimester and 1,475 exposed in the second/third trimester), there was no increase in overall major birth defects with TDF compared with the background birth defect rate of 2.7% in a U.S. reference population of the MACDP. The prevalence of major birth defects in live births was 2.3% (95% CI: 1.8% to 2.8%) with first trimester exposure to TDF-containing regimens, and 2.1% (95% CI: 1.4% to 3.0%) with the second/third trimester exposure to TDF-containing regimens.

Prospective reports from the APR of overall major birth defects in pregnancies exposed to TDF are compared with a U.S. background major birth defect rate. Methodological limitations of the APR include the use of MACDP as the external comparator group. Limitations of using an external comparator include differences in methodology and populations, as well as confounding due to the underlying disease.

In published data from three controlled clinical trials, a total of 327 pregnant women with chronic HBV infection were administered tenofovir disoproxil fumarate from 28 to 32 weeks gestation through 1 to 2 months postpartum and followed for up to 12 months after delivery. There were no new safety findings in pregnant women compared with the known safety profile of tenofovir disoproxil fumarate in HBV-infected adults. An increased risk of adverse pregnancy-related outcomes was not observed; 2 stillbirths were identified, and there was 1 major birth defect (talipes) and 1 occurrence of multiple congenital abnormalities (not further specified) in tenofovir disoproxil fumarate-exposed infants. Infants were followed for up to 12 months after delivery; there were no clinically relevant drug-related safety findings in infants exposed to tenofovir disoproxil fumarate during late gestation.

Animal Data

Efavirenz

Effects of EFV on embryo-fetal development have been studied in three nonclinical species (cynomolgus monkeys, rats, and rabbits). In monkeys, EFV 60 mg/kg/day was administered to pregnant females throughout pregnancy (gestation days 20 through 150). The maternal systemic drug exposures (AUC) were 1.3 times the exposure in humans at the recommended clinical dose (600 mg/day), with fetal umbilical venous drug concentrations approximately 0.7 times the maternal values. Three of 20 fetuses/infants had one or more malformations; there were no malformed fetuses or infants from placebo-treated mothers. The malformations that occurred in these three monkey fetuses included anencephaly and unilateral anophthalmia in one fetus, microophthalmia in a second, and cleft palate in the third. There was no NOAEL (no observable adverse effect level) established for this study because only one dosage was evaluated. In rats, EFV was administered either during organogenesis (gestation days 7 to 18) or from gestation day 7 through lactation day 21 at 50, 100, or 200 mg/kg/day. Administration of 200 mg/kg/day in rats was associated with increase in the incidence of early resorptions; and doses 100 mg/kg/day and greater were associated with early neonatal mortality. The AUC at the NOAEL (50 mg/kg/day) in this rat study was 0.1 times that in humans at the recommended clinical dose. Drug concentrations in the milk on lactation day 10 were approximately 8 times higher than those in maternal plasma. In pregnant rabbits, EFV was neither embryo lethal nor teratogenic when administered at doses of 25, 50, and 75 mg/kg/day over the period of organogenesis (gestation days 6 through 18). The AUC at the NOAEL (75 mg/kg/day) in rabbits was 0.4 times that in humans at the recommended clinical dose.

Lamivudine

3TC was administered orally to pregnant rats (at 90, 600, and 4,000 mg per kg per day) and rabbits (at 90, 300, and 1,000 mg per kg per day and at 15, 40, and 90 mg per kg per day) during organogenesis (on gestation Days 7 through 16 [rat] and 8 through 20 [rabbit]). No evidence of fetal malformations due to 3TC was observed in rats and rabbits at doses producing plasma concentrations (Cmax) approximately 35 times higher than human exposure at the recommended daily dose. Evidence of early embryolethality was seen in the rabbit at system exposures (AUC) similar to those observed in humans, but there was no indication of this effect in the rat at plasma concentrations (Cmax) 35 times higher than human exposure at the recommended daily dose. Studies in pregnant rats showed that 3TC is transferred to the fetus through the placenta. In the fertility/pre- and postnatal development study in rats, 3TC was administered orally at doses of 180, 900, and 4,000 mg per kg per day (from prior to mating through postnatal Day 20). In the study, development of the offspring, including fertility and reproductive performance, was not affected by maternal administration of 3TC.

Tenofovir Disoproxil Fumarate

TDF was administered orally to pregnant rats (at 0, 50, 150, or 450 mg/kg/day) and rabbits (at 0, 30, 100, or 300 mg/kg/day) through organogenesis (on gestation days 7 through 17, and 6 through 18, respectively). No significant toxicological effects were observed in embryo-fetal toxicity studies performed with TDF in rats at doses up to 14 times the human dose based on body surface area comparisons and in rabbits at doses up to 19 times the human dose based on body surface area comparisons. In a pre/postnatal development study in rats, TDF was administered orally through lactation at doses up to 600 mg/kg/day; no adverse effects were observed in the offspring at tenofovir exposures of approximately 2.7 times higher than human exposures at the recommended daily dose of TDF.

8.2 Lactation

Risk Summary

The Centers for Disease Control and Prevention recommend that HIV-1-infected mothers not breastfeed their infants to avoid risking postnatal transmission of HIV-1 infection.

Efavirenz

EFV has been shown to pass into human breast milk. There is no information available on the effects of EFV on the breastfed infant, or the effects of EFV on milk production.

Lamivudine

3TC is present in human milk. Samples of breast milk obtained from 20 mothers receiving 3TC monotherapy, 300 mg twice daily (2 times the dose in SYMFI), had measurable concentrations of 3TC. There is no information on the effects of 3TC on the breastfed infant, or the effects of 3TC on milk production.

Tenofovir Disoproxil Fumarate

Based on published data, tenofovir has been shown to be present in human breast milk (see Data). It is not known if tenofovir affects milk production or has effects on the breastfed child.

Because of the potential for (1) HIV transmission (in HIV-negative infants); (2) developing viral resistance (in HIV-positive infants); and (3) adverse reactions in a breastfed infant similar to those seen in adults, instruct mothers not to breastfeed if they are receiving SYMFI.

Data

Tenofovir Disoproxil Fumarate

In a study of 50 HIV-uninfected, breastfeeding women on a tenofovir-containing regimen initiated between 1 and 24 weeks postpartum (median 13 weeks), tenofovir was undetectable in the plasma of most infants after 7 days of treatment in mothers. There were no serious adverse events in mothers or infants.

8.3 Females and Males of Reproductive Potential

Because of potential teratogenic effects, pregnancy should be avoided in women receiving SYMFI [see Warnings and Precautions (5.7), Use in Specific Populations (8.1)].

Pregnancy Testing

Females of reproductive potential should undergo pregnancy testing before initiation of SYMFI.

Contraception

Females of reproductive potential should use effective contraception during treatment with SYMFI and for 12 weeks after discontinuing SYMFI due to the long half-life of EFV. Barrier contraception should always be used in combination with other methods of contraception. Hormonal methods that contain progesterone may have decreased effectiveness [see Drug Interactions (7.5)].

8.4 Pediatric Use

The safety and effectiveness of SYMFI as a fixed-dose tablet in pediatric patients infected with HIV-1 and weighing at least 40 kg have been established based on clinical studies using the individual components (efavirenz, lamivudine, and tenofovir disoproxil fumarate).

8.5 Geriatric Use

Clinical studies of SYMFI did not include sufficient numbers of subjects aged 65 and over to determine whether they respond differently from younger subjects. In general, caution should be exercised in the administration of 3TC in elderly patients reflecting the greater frequency of decreased hepatic, renal, or cardiac function, and of concomitant disease or other drug therapy.

8.6 Renal Impairment

SYMFI is not recommended for patients with impaired renal function (i.e., creatinine clearance less than 50 mL/min) or patients with end-stage renal disease (ESRD) requiring hemodialysis because it is a fixed-dose combination formulation that cannot be adjusted [see Dosage and Administration (2.3)].

8.7 Hepatic Impairment

SYMFI is not recommended for patients with moderate or severe hepatic impairment because there are insufficient data to determine whether dose adjustment is necessary. Patients with mild hepatic impairment may be treated with SYMFI without any adjustment in dose [see Dosage and Administration (2.4), Warnings and Precautions (5.9) and Clinical Pharmacology (12.3)].

10 OVERDOSAGE

If overdose occurs, the patient must be monitored for evidence of toxicity, and standard supportive treatment applied as necessary.

Efavirenz: Some patients accidentally taking 600 mg twice daily have reported increased nervous system symptoms. One patient experienced involuntary muscle contractions.

Treatment of overdose with EFV should consist of general supportive measures, including monitoring of vital signs and observation of the patient’s clinical status. Administration of activated charcoal may be used to aid removal of unabsorbed drug. There is no specific antidote for overdose with efavirenz. Since efavirenz is highly protein bound, dialysis is unlikely to significantly remove the drug from blood.

Lamivudine: There is no known specific treatment for overdose with 3TC. If overdose occurs, the patient should be monitored and standard supportive treatment applied as required because a negligible amount of 3TC was removed via (4-hour) hemodialysis, continuous ambulatory peritoneal dialysis, and automated peritoneal dialysis, it is not known if continuous hemodialysis would provide clinical benefit in a 3TC overdose event.

Tenofovir Disoproxil Fumarate: Limited clinical experience at doses higher than the therapeutic dose of TDF 300 mg is available.

Tenofovir is efficiently removed by hemodialysis with an extraction coefficient of approximately 54%. Following a single 300 mg dose of tenofovir disoproxil fumarate, a 4-hour hemodialysis session removed approximately 10% of the administered tenofovir dose.

11 DESCRIPTION

SYMFI tablets contain efavirenz (EFV), an HIV-1 specific, non-nucleoside, reverse transcriptase inhibitor (NNRTI), lamivudine (also known as 3TC), a synthetic nucleoside analogue with activity against HIV-1 and tenofovir disoproxil fumarate (TDF) (a prodrug of tenofovir), a fumaric acid salt of bis-isopropoxycarbonyloxymethyl ester derivative of tenofovir. TDF is converted in vivo to tenofovir, an acyclic nucleoside phosphonate (nucleotide) analog of adenosine 5’-monophosphate. Tenofovir exhibits activity against HIV-1 reverse transcriptase.

SYMFI tablets are for oral administration. Each film-coated tablet contains 600 mg of efavirenz, 300 mg of lamivudine and 300 mg of tenofovir disoproxil fumarate, which is equivalent to 245 mg of tenofovir disoproxil, and the following inactive ingredients: croscarmellose sodium, hydroxypropyl cellulose, lactose monohydrate, magnesium stearate, microcrystalline cellulose, polyethylene glycol, polyvinyl alcohol, sodium chloride, sodium lauryl sulfate, talc and titanium dioxide.

Efavirenz: The chemical name of efavirenz is (4S)-6-chloro-4-(cyclopropylethynyl)-1,4-dihydro-4-(trifluoromethyl)-2H-3,1-benzoxazin-2-one. Its molecular formula is C14H9ClF3NO2 and its structural formula is:

Efavirenz is a white to slightly pink crystalline powder with a molecular mass of 315.68. It is soluble in methanol and practically insoluble in water (< 10 microgram/mL).

Lamivudine: The chemical name of lamivudine is (-)-1-[(2R,5S)-2-(Hydroxymethyl)-1,3-oxathiolan-5-yl]cytosine. Lamivudine is the (-)enantiomer of a dideoxy analogue of cytidine. Lamivudine has also been referred to as (-)2′,3′-dideoxy, 3′-thiacytidine. It has a molecular formula of C8H11N3O3S and a molecular weight of 229.26 g per mol. It has the following structural formula:

Lamivudine is a white to off-white solid with a solubility of approximately 70 mg per mL in water at 20°C.

Tenofovir Disoproxil Fumarate: The chemical name of tenofovir DF is 9-[(R)-2-[[Bis[[(isopropoxycarbonyl)oxy]methoxy]phosphinyl]methoxy]propyl]adenine fumarate (1:1). It has a molecular formula of C19H30N5O10P•C4H4O4 and a molecular weight of 635.51. It has the following structural formula:

Tenofovir DF is a white to off-white powder with a solubility of 13.4 mg/mL in distilled water at 25°C. It has an octanol/phosphate buffer (pH 6.5) partition coefficient (log p) of 1.25 at 25°C.

12 CLINICAL PHARMACOLOGY

12.1 Mechanism of Action

SYMFI is a fixed-dose combination of antiviral drugs EFV, 3TC, and TDF with antiviral activity against HIV-1 [see Microbiology (12.4)].

12.2 Pharmacodynamics

Cardiac Electrophysiology

The effect of EFV on the QTc interval was evaluated in an open-label, positive and placebo-controlled, fixed single sequence 3-period, 3-treatment crossover QT study in 58 healthy subjects enriched for CYP2B6 polymorphisms. The mean Cmax of EFV in subjects with CYP2B6 *6/*6 genotype following the administration of 600 mg daily dose for 14 days was 2.25-fold the mean Cmax observed in subjects with CYP2B6 *1/*1 genotype. A positive relationship between EFV concentration and QTc prolongation was observed. Based on the concentration-QTc relationship, the mean QTc prolongation and its upper bound 90% confidence interval are 8.7 ms and 11.3 ms in subjects with CYP2B6*6/*6 genotype following the administration of 600 mg daily dose for 14 days [see Warnings and Precautions (5.16)].

12.3 Pharmacokinetics

The effect of food on SYMFI has not been evaluated.

Efavirenz

In HIV-1-infected subjects, time-to-peak plasma concentrations were approximately 3 to 5 hours and steady-state plasma concentrations were reached in 6 to 10 days. EFV is highly bound (approximately 99.5 to 99.75%) to human plasma proteins, predominantly albumin. Following administration of ^14C-labeled EFV, 14 to 34% of the dose was recovered in the urine (mostly as metabolites) and 16 to 61% was recovered in feces (mostly as parent drug). In vitro studies suggest CYP3A and CYP2B6 are the major isozymes responsible for EFV metabolism. EFV has been shown to induce CYP enzymes, resulting in induction of its own metabolism. EFV has a terminal half-life of 52 to 76 hours after single doses and 40 to 55 hours after multiple doses.

Lamivudine

After oral administration of 2 mg/kg of 3TC twice a day to 9 adults with HIV-1, the peak serum 3TC concentration (Cmax) was 1.5 ± 0.5 mcg/mL (mean ± SD). The area under the plasma concentration versus time curve (AUC) and Cmax increased in proportion to oral dose over the range from 0.25 to 10 mg/kg and absolute bioavailability in 12 adult patients was 86% ± 16% (mean ± SD) for the 150-mg tablet and 87% ± 13% for the oral solution. Binding of 3TC to human plasma proteins is low (< 36%). Within 12 hours after a single oral dose of 3TC in 6 HIV-1-infected adults, 5.2% ± 1.4% (mean ± SD) of the dose was excreted as the trans-sulfoxide metabolite in the urine. The majority of 3TC is eliminated unchanged in urine by active organic cationic secretion and the observed mean elimination half-life (t1/2) ranged from 5 to 7 hours in most single-dose studies with serum sampling for 24 hours after dosing.

Tenofovir Disoproxil Fumarate

Following oral administration of a single 300 mg dose of TDF to HIV-1-infected subjects in the fasted state, maximum serum concentrations (Cmax) were achieved in 1.0 ± 0.4 hrs (mean ± SD) and Cmax and AUC values were 296 ± 90 ng/mL and 2287 ± 685 ng•hr/mL, respectively. The oral bioavailability of tenofovir from TDF in fasted subjects is approximately 25%. Less than 0.7% of tenofovir binds to human plasma proteins in vitro and the binding is independent of concentration over the range of 0.01 to 25 mcg/mL. Approximately 70 to 80% of the intravenous dose of tenofovir is recovered as unchanged drug in the urine. Tenofovir is eliminated by a combination of glomerular filtration and active tubular secretion with a renal clearance in adults with normal renal function of 243 ± 33 mL/min (mean ± SD). Following a single oral dose, the terminal elimination half-life of tenofovir is approximately 17 hours.

Special Populations

Race

Efavirenz and Lamivudine

There are no significant or clinically relevant racial differences in EFV and 3TC pharmacokinetics.

Tenofovir Disoproxil Fumarate

There were insufficient numbers from racial and ethnic groups other than Caucasian to adequately determine potential pharmacokinetic differences among these populations.

Gender

There are no significant or clinically relevant gender differences in the pharmacokinetics of EFV, 3TC, and TDF.

Geriatric Patients

The pharmacokinetics of 3TC and TDF have not been studied in patients over 65 years of age.

Patients with Renal Impairment

[See Use in Specific Populations (8.6).]

Efavirenz

The pharmacokinetics of EFV have not been studied in patients with renal impairment.

Lamivudine

The pharmacokinetics of 3TC are altered in subjects with renal impairment (Table 4).

Table 4. Pharmacokinetic Parameters (Mean ± SD) After a Single 300-mg Oral Dose of 3TC in Subjects with Varying Degrees of Renal Function
Parameter | Creatinine Clearance Criterion (Number of Subjects)
Parameter | > 60 mL/min; (n = 6) | 10-30 mL/min; (n = 4) | < 10 mL/min; (n = 6)
Creatinine clearance (mL/min) | 111 ± 14 | 28 ± 8 | 6 ± 2
Cmax (mcg/mL) | 2.6 ± 0.5 | 3.6 ± 0.8 | 5.8 ± 1.2
AUC∞ (mcg•h/mL) | 11.0 ± 1.7 | 48.0 ± 19 | 157 ± 74
Cl/F (mL/min) | 464 ± 76 | 114 ± 34 | 36 ± 11

Tenofovir Disoproxil Fumarate

The pharmacokinetics of TDF are altered in subjects with renal impairment [see Warnings and Precautions (5.4)]. In subjects with creatinine clearance below 50 mL/min or with end‑stage renal disease (ESRD) requiring dialysis, Cmax, and AUC0‑∞ of tenofovir were increased.

Table 5. Pharmacokinetic Parameters (Mean ± SD) of Tenofovir After a Single 300-mg Oral Dose of TDF in Subjects with Varying Degrees of Renal Function
Baseline Creatinine Clearance (mL/min) | > 80; (N = 3) | 50-80; (N = 10) | 30-49; (N = 8) | 12-29; (N = 11)
Cmax (µg/mL) | 0.34 ± 0.03 | 0.33 ± 0.06 | 0.37 ± 0.16 | 0.60 ± 0.19
AUC0-∞ (µg•hr/mL) | 2.18 ± 0.26 | 3.06 ± 0.93 | 6.01 ± 2.50 | 15.98 ± 7.22
CL/F (mL/min) | 1043.7 ± 115.4 | 807.7 ± 279.2 | 444.4 ± 209.8 | 177.0 ± 97.1
CLrenal (mL/min) | 243.5 ± 33.3 | 168.6 ± 27.5 | 100.6 ± 27.5 | 43.0 ± 31.2

Patients with Hepatic Impairment

Efavirenz

A multiple-dose study showed no significant effect on EFV pharmacokinetics in patients with mild hepatic impairment (Child-Pugh Class A) compared with controls. There were insufficient data to determine whether moderate or severe hepatic impairment (Child-Pugh Class B or C) affects EFV pharmacokinetics.

Lamivudine

The pharmacokinetic properties of 3TC have been determined in adults with impaired hepatic function. Pharmacokinetic parameters were not altered by diminishing hepatic function. Safety and efficacy of 3TC have not been established in the presence of decompensated liver disease.

Tenofovir Disoproxil Fumarate

The pharmacokinetics of tenofovir following a 300 mg single dose of TDF have been studied in non-HIV infected subjects with moderate to severe (Child-Pugh B to C) hepatic impairment. There were no substantial alterations in tenofovir pharmacokinetics in subjects with hepatic impairment compared with unimpaired subjects.

Assessment of Drug Interactions

[See Drug Interactions (7).]

Efavirenz

EFV has been shown in vivo to cause hepatic enzyme induction, thus increasing the biotransformation of some drugs metabolized by CYP3A and CYP2B6. In vitro studies have shown that EFV inhibited CYP isozymes 2C9, 2C19, and 3A4 with Ki values (8.5 to 17 µM) in the range of observed EFV plasma concentrations. In in vitro studies, EFV did not inhibit CYP2E1 and inhibited CYP2D6 and CYP1A2 (Ki values 82 to 160 µM) only at concentrations well above those achieved clinically. Coadministration of EFV with drugs primarily metabolized by 2C9, 2C19, and 3A isozymes may result in altered plasma concentrations of the coadministered drug. Drugs which induce CYP3A activity would be expected to increase the clearance of EFV resulting in lowered plasma concentrations.

Drug interaction studies were performed with EFV and other drugs likely to be coadministered or drugs commonly used as probes for pharmacokinetic interaction. The effects of coadministration of EFV on the Cmax, AUC, and Cmin are summarized in Table 6 (effect of EFV on other drugs) and Table 7 (effect of other drugs on EFV). For information regarding clinical recommendations see Drug Interactions (7.5).

Table 6. Effect of Efavirenz on Coadministered Drug Plasma Cmax, AUC, and Cmin
 |  |  | Number of Subjects | Coadministered Drug (mean % change)
Coadministered Drug | Dose | Efavirenz Dose | Number of Subjects | Cmax (90% CI) | AUC (90% CI) | Cmin (90% CI)
Boceprevir | 800 mg tid x 6 days | 600 mg qd x 16 days | NA | ↓ 8%; (↓ 22-↑ 8%) | ↓ 19%; (11-25%) | ↓ 44%; (26-58%)
Simeprevir | 150 mg qd x 14 days | 600 mg qd x 14 days | 23 | ↓ 51%; (↓ 46-↓ 56%) | ↓ 71%; (↓ 67-↓ 74%) | ↓ 91%; (↓ 88-↓ 92%)
Ledipasvir/; Sofosbuvir [Study conducted with ATRIPLA® coadministered with HARVONI®.] | 90/400 mg qd x 14 days | 600 mg qd x 14 days | 15 | ↓ 34; (↓ 25-↓ 41) | ↓ 34; (↓ 25-↓ 41) | ↓ 34; (↓ 24-↓ 43)
Ledipasvir |  |  |  | ↔ | ↔ | NA
Sofosbuvir; GS-331007 [The predominant circulating nucleoside metabolite of sofosbuvir.] |  |  |  | ↔ | ↔ | ↔
Sofosbuvir [Study conducted with ATRIPLA coadministered with SOVALDI® (sofosbuvir).] | 400 mg qd single dose | 600 mg qd x 14 days | 16 | ↓ 19; (↓ 40-↑ 10) | ↔ | NA
GS-331007 |  |  |  | ↓ 23; (↓ 16-↓ 30) | ↓ 16; (↓ 24-↓ 8) | NA
Sofosbuvir/; Velpatasvir [Study conducted with ATRIPLA coadministered with EPCLUSA®.]; Sofosbuvir; GS-331007; Velpatasvir | 400/100 mg qd x 14 days | 600 mg qd x 14 days | 14
Sofosbuvir/; Velpatasvir [Study conducted with ATRIPLA coadministered with EPCLUSA®.]; Sofosbuvir; GS-331007; Velpatasvir | 400/100 mg qd x 14 days | 600 mg qd x 14 days | 14 | ↑ 38; (↑ 14-↑ 67) | ↔ | NA
Sofosbuvir/; Velpatasvir [Study conducted with ATRIPLA coadministered with EPCLUSA®.]; Sofosbuvir; GS-331007; Velpatasvir | 400/100 mg qd x 14 days | 600 mg qd x 14 days | 14 | ↓ 14; (↓ 20-↓ 7) | ↔ | ↔
Sofosbuvir/; Velpatasvir [Study conducted with ATRIPLA coadministered with EPCLUSA®.]; Sofosbuvir; GS-331007; Velpatasvir | 400/100 mg qd x 14 days | 600 mg qd x 14 days | 14 | ↓ 47; (↓ 57-↓ 36) | ↓ 53; (↓ 61-↓ 43) | ↓ 57; (↓ 64-↓ 48)
Azithromycin | 600 mg single dose | 400 mg qd x 7 days | 14 | ↑ 22%; (4-42%) | ↔ | NA
Clarithromycin | 500 mg q12h x 7 days | 400 mg qd x 7 days | 11 | ↓ 26%; (15-35%) | ↓ 39%; (30-46%) | ↓ 53%; (42-63%)
14-OH metabolite |  |  |  | ↑ 49%; (32-69%) | ↑ 34%; (18-53%) | ↑ 26%; (9-45%)
Fluconazole | 200 mg x 7 days | 400 mg qd x 7 days | 10 | ↔ | ↔ | ↔
Itraconazole | 200 mg q12h x 28 days | 600 mg qd x 14 days | 18 | ↓ 37%; (20-51%) | ↓ 39%; (21-53%) | ↓ 44%; (27-58%)
Hydroxy-itraconazole |  |  |  | ↓ 35%; (12-52%) | ↓ 37%; (14-55%) | ↓ 43%; (18-60%)
Posaconazole | 400 mg (oral suspension) bid x 10 and 20 days | 400 mg qd x 10 and 20 days | 11 | ↓ 45%; (34-53%) | ↓ 50%; (40-57%) | NA
Rifabutin | 300 mg qd x 14 days | 600 mg qd x 14 days | 9 | ↓ 32%; (15-46%) | ↓ 38%; (28-47%) | ↓ 45%; (31-56%)
Voriconazole | 400 mg po q12h x 1 day, then 200 mg po q12h x 8 days | 400 mg qd x 9 days | NA | ↓ 61% [90% CI not available.] | ↓ 77% | NA
 | 300 mg po q12h days 2‑7 | 300 mg qd x 7 days | NA | ↓ 36% [Relative to steady-state administration of voriconazole (400 mg for 1 day, then 200 mg po q12h for 2 days).]; (21-49%) | ↓ 55%; (45-62%) | NA
 | 400 mg po q12h days 2‑7 | 300 mg qd x 7 days | NA | ↑ 23%; (↓ 1-↑ 53%) | ↓ 7%; (↓ 23-↑ 13%) | NA
Artemether/; lumefantrine | Artemether 20 mg/ lumefantrine 120 mg tablets (6 4-tablet doses over 3 days) | 600 mg qd x 26 days | 12
Artemether | Artemether 20 mg/ lumefantrine 120 mg tablets (6 4-tablet doses over 3 days) | 600 mg qd x 26 days |  | ↓ 21% | ↓ 51% | NA
dihydroartemisinin | Artemether 20 mg/ lumefantrine 120 mg tablets (6 4-tablet doses over 3 days) | 600 mg qd x 26 days |  | ↓ 38% | ↓ 46% | NA
lumefantrine | Artemether 20 mg/ lumefantrine 120 mg tablets (6 4-tablet doses over 3 days) | 600 mg qd x 26 days |  | ↔ | ↓ 21% | NA
Atorvastatin | 10 mg qd x 4 days | 600 mg qd x 15 days | 14 | ↓ 14%; (1-26%) | ↓ 43%; (34-50%) | ↓ 69%; (49-81%)
Total active (including metabolites) |  |  |  | ↓ 15%; (2-26%) | ↓ 32%; (21-41%) | ↓ 48%; (23-64%)
Pravastatin | 40 mg qd x 4 days | 600 mg qd x 15 days | 13 | ↓ 32%; (↓ 59-↑ 12%) | ↓ 44%; (26-57%) | ↓ 19%; (0-35%)
Simvastatin | 40 mg qd x 4 days | 600 mg qd x 15 days | 14 | ↓ 72%; (63-79%) | ↓ 68%; (62-73%) | ↓ 45%; (20-62%)
Total active (including metabolites) |  |  |  | ↓ 68%; (55-78%) | ↓ 60%; (52-68%) | NA [Not available because of insufficient data.]
Carbamazepine | 200 mg qd x 3 days, 200 mg bid x 3 days, then 400 mg qd x 29 days | 600 mg qd x 14 days | 12 | ↓ 20%; (15-24%) | ↓ 27%; (20-33%) | ↓ 35%; (24-44%)
Epoxide metabolite |  |  |  | ↔ | ↔ | ↓ 13%; (↓ 30-↑ 7%)
Cetirizine | 10 mg single dose | 600 mg qd x 10 days | 11 | ↓ 24%; (18-30%) | ↔ | NA
Diltiazem | 240 mg x 21 days | 600 mg qd x 14 days | 13 | ↓ 60%; (50-68%) | ↓ 69%; (55-79%) | ↓ 63%; (44-75%)
Desacetyl diltiazem |  |  |  | ↓ 64%; (57-69%) | ↓ 75%; (59-84%) | ↓ 62%; (44-75%)
N-monodes-methyl diltiazem |  |  |  | ↓ 28%; (7-44%) | ↓ 37%; (17-52%) | ↓ 37%; (17-52%)
Ethinyl estradiol/ Norgestimate | 0.035 mg/0.25 mg x 14 days | 600 mg qd x 14 days
Ethinyl estradiol |  |  | 21 | ↔ | ↔ | ↔
Norelgestromine |  |  | 21 | ↓ 46%; (39-52%) | ↓ 64%; (62-67%) | ↓ 82%; (79-85%)
Levonorgestrel |  |  | 6 | ↓ 80%; (77-83%) | ↓ 83%; (79-87%) | ↓ 86%; (80-90%)
Lorazepam | 2 mg single dose | 600 mg qd x 10 days | 12 | ↑ 16%; (2-32%) | ↔ | NA
Methadone | Stable maintenance 35‑100 mg daily | 600 mg qd x 14‑21 days | 11 | ↓ 45%; (25-59%) | ↓ 52%; (33-66%) | NA
Bupropion | 150 mg single dose (sustained-release) | 600 mg qd x 14 days | 13 | ↓ 34%; (21-47%) | ↓ 55%; (48-62%) | NA
Hydroxy-bupropion |  |  |  | ↑ 50%; (20-80%) | ↔ | NA
Paroxetine | 20 mg qd x 14 days | 600 mg qd x 14 days | 16 | ↔ | ↔ | ↔
Sertraline | 50 mg qd x 14 days | 600 mg qd x 14 days | 13 | ↓ 29%; (15-40%) | ↓ 39%; (27-50%) | ↓ 46%; (31-58%)
↑ Indicates increase ↓ Indicates decrease ↔ Indicates no change or a mean increase or decrease of < 10%.
NA = not available.

Table 7. Effect of Coadministered Drug on Efavirenz Plasma Cmax, AUC, and Cmin
 |  |  | Number of Subjects | Efavirenz (mean % change)
Coadministered Drug | Dose | Efavirenz Dose | Number of Subjects | Cmax (90% CI) | AUC (90% CI) | Cmin (90% CI)
Boceprevir | 800 mg tid x 6 days | 600 mg qd x 16 days | NA | ↑ 11%; (2-20%) | ↑ 20%; (15-26%) | NA
Simeprevir | 150 mg qd x 14 days | 600 mg qd x 14 days | 23 | ↔ | ↓ 10%; (5-15%) | ↓ 13%; (7-19%)
Azithromycin | 600 mg single dose | 400 mg qd x 7 days | 14 | ↔ | ↔ | ↔
Clarithromycin | 500 mg q12h x 7 days | 400 mg qd x 7 days | 12 | ↑ 11%; (3-19%) | ↔ | ↔
Fluconazole | 200 mg x 7 days | 400 mg qd x 7 days | 10 | ↔ | ↑ 16%; (6-26%) | ↑ 22%; (5-41%)
Itraconazole | 200 mg q12h x 14 days | 600 mg qd x 28 days | 16 | ↔ | ↔ | ↔
Rifabutin | 300 mg qd x 14 days | 600 mg qd x 14 days | 11 | ↔ | ↔ | ↓ 12%; (↓ 24-↑ 1%)
Rifampin | 600 mg x 7 days | 600 mg qd x 7 days | 12 | ↓ 20%; (11-28%) | ↓ 26%; (15-36%) | ↓ 32%; (15-46%)
Voriconazole | 400 mg po q12h x 1 day, then 200 mg po q12h x 8 days | 400 mg qd x 9 days | NA | ↑ 38% [90% CI not available.] | ↑ 44% | NA
Voriconazole | 300 mg po q12h days 2-7 | 300 mg qd x 7 days | NA | ↓ 14% [Relative to steady-state administration of efavirenz (600 mg once daily for 9 days).]; (7-21%) | ↔ | NA
Voriconazole | 400 mg po q12h days 2-7 | 300 mg qd x 7 days | NA | ↔ | ↑ 17%; (6-29%) | NA
Artemether/; Lumefantrine | Artemether 20 mg/ lumefantrine 120 mg tablets (6 4-tablet doses over 3 days) | 600 mg qd x 26 days | 12 | ↔ | ↓ 17% | NA
Atorvastatin | 10 mg qd x 4 days | 600 mg qd x 15 days | 14 | ↔ | ↔ | ↔
Pravastatin | 40 mg qd x 4 days | 600 mg qd x 15 days | 11 | ↔ | ↔ | ↔
Simvastatin | 40 mg qd x 4 days | 600 mg qd x 15 days | 14 | ↓ 12%; (↓ 28-↑ 8%) | ↔ | ↓ 12%; (↓ 25-↑ 3%)
Aluminum hydroxide 400 mg, magnesium hydroxide 400 mg, plus simethicone 40 mg | 30 mL single dose | 400 mg single dose | 17 | ↔ | ↔ | NA
Carbamazepine | 200 mg qd x 3 days, 200 mg bid x 3 days, then 400 mg qd x 15 days | 600 mg qd x 35 days | 14 | ↓ 21%; (15-26%) | ↓ 36%; (32-40%) | ↓ 47%; (41-53%)
Cetirizine | 10 mg single dose | 600 mg qd x 10 days | 11 | ↔ | ↔ | ↔
Diltiazem | 240 mg x 14 days | 600 mg qd x 28 days | 12 | ↑ 16%; (6-26%) | ↑ 11%; (5-18%) | ↑ 13%; (1-26%)
Famotidine | 40 mg single dose | 400 mg single dose | 17 | ↔ | ↔ | NA
Paroxetine | 20 mg qd x 14 days | 600 mg qd x 14 days | 12 | ↔ | ↔ | ↔
Sertraline | 50 mg qd x 14 days | 600 mg qd x 14 days | 13 | ↑ 11%; (6-16%) | ↔ | ↔
↑ Indicates increase ↓ Indicates decrease ↔ Indicates no change or a mean increase or decrease of < 10%.
NA = not available.

Lamivudine

Effect of 3TC on the Pharmacokinetics of Other Agents

Based on in vitro study results, 3TC at therapeutic drug exposures is not expected to affect the pharmacokinetics of drugs that are substrates of the following transporters: organic anion transporter polypeptide 1B1/3 (OATP1B1/3), breast cancer resistance protein (BCRP), P-glycoprotein (P-gp), multidrug and toxin extrusion protein 1 (MATE1), MATE2-K, organic cation transporter 1 (OCT1), OCT2, or OCT3.

Effect of Other Agents on the Pharmacokinetics of 3TC

3TC is a substrate of MATE1, MATE2-K, and OCT2 in vitro. Trimethoprim (an inhibitor of these drug transporters) has been shown to increase 3TC plasma concentrations. This interaction is not considered clinically significant as no dose adjustment of 3TC is needed.

3TC is a substrate of P-gp and BCRP; however, considering its absolute bioavailability (87%), it is unlikely that these transporters play a significant role in the absorption of 3TC. Therefore, coadministration of drugs that are inhibitors of these efflux transporters is unlikely to affect the disposition and elimination of 3TC.

Interferon Alfa

There was no significant pharmacokinetic interaction between 3TC and interferon alfa in a trial of 19 healthy male subjects.

Ribavirin

In vitro data indicate ribavirin reduces phosphorylation of 3TC, stavudine, and zidovudine. However, no pharmacokinetic (e.g., plasma concentrations or intracellular triphosphorylated active metabolite concentrations) or pharmacodynamic (e.g., loss of HIV-1/HCV virologic suppression) interaction was observed when ribavirin and 3TC (n = 18), stavudine (n = 10), or zidovudine (n = 6) were coadministered as part of a multi-drug regimen to HIV-1/HCV co-infected subjects.

Sorbitol (Excipient)

3TC and sorbitol solutions were coadministered to 16 healthy adult subjects in an open-label, randomized-sequence, 4-period, crossover trial. Each subject received a single 300-mg dose of 3TC oral solution alone or coadministered with a single dose of 3.2 grams, 10.2 grams, or 13.4 grams of sorbitol in solution. Coadministration of 3TC with sorbitol resulted in dose-dependent decreases of 20%, 39%, and 44% in the AUC(0-24), 14%, 32%, and 36% in the AUC(∞), and 28%, 52%, and 55% in the Cmax of lamivudine, respectively.

Trimethoprim/Sulfamethoxazole

3TC and TMP/SMX were coadministered to 14 HIV-1-positive subjects in a single-center, open-label, randomized, crossover trial. Each subject received treatment with a single 300-mg dose of 3TC and TMP 160 mg/SMX 800 mg once a day for 5 days with concomitant administration of 3TC 300 mg with the fifth dose in a crossover design. Coadministration of TMP/SMX with 3TC resulted in an increase of 43% ± 23% (mean ± SD) in 3TC AUC∞, a decrease of 29% ± 13% in 3TC oral clearance, and a decrease of 30% ± 36% in 3TC renal clearance. The pharmacokinetic properties of TMP and SMX were not altered by coadministration with 3TC. There is no information regarding the effect on 3TC pharmacokinetics of higher doses of TMP/SMX such as those used in treating PCP.

Tenofovir Disoproxil Fumarate

At concentrations substantially higher (~300-fold) than those observed in vivo, tenofovir did not inhibit in vitro CYP3A4, CYP2D6, CYP2C9, or CYP2E1. However, a small (6%) but statistically significant reduction in metabolism of CYP1A substrate was observed. Based on the results of in vitro experiments and the known elimination pathway of tenofovir, the potential for CYP mediated interactions involving TDF with other medicinal products is low.

Table 8 summarizes pharmacokinetic effects of coadministered drug on tenofovir pharmacokinetics. No clinically significant drug interactions have been observed between tenofovir and ribavirin.

Table 8. Drug Interactions: Changes in Pharmacokinetic Parameters for Tenofovir [Subjects received tenofovir disoproxil fumarate 300 mg once daily.] in the Presence of the Coadministered Drug
Coadministered Drug | Dose of Coadministered Drug (mg) | N | % Change of Tenofovir Pharmacokinetic Parameters [Increase = ↑; Decrease = ↓; No Effect = ↔; NC = Not Calculated]; (90% CI)
Coadministered Drug | Dose of Coadministered Drug (mg) | N | Cmax | AUC | Cmin
Ledipasvir/; Sofosbuvir [Data generated from simultaneous dosing with ledipasvir/sofosbuvir. Staggered administration (12 hours apart) provide similar results.] [Comparison based on exposures when administered as atazanavir/ritonavir + emtricitabine/tenofovir DF.] | 90/400 once daily x 10 days | 24 | ↑ 47; (↑ 37 to ↑ 58) | ↑ 35; (↑ 29 to ↑ 42) | ↑ 47; (↑ 38 to ↑ 57)
Ledipasvir/; Sofosbuvir [Comparison based on exposures when administered as darunavir/ritonavir + emtricitabine/tenofovir DF.] | 90/400 once daily x 10 days | 23 | ↑ 64; (↑ 54 to ↑ 74) | ↑ 50; (↑ 42 to ↑ 59) | ↑ 59; (↑ 49 to ↑ 70)
Ledipasvir/; Sofosbuvir [Study conducted with efavirenz/emtricitabine/tenofovir disoproxil fumarate coadministered with ledipasvir/sofosbuvir.] | 90/400 once daily x 14 days | 15 | ↑ 79; (↑ 56 to ↑ 104) | ↑ 98; (↑ 77 to ↑ 123) | ↑ 163; (↑ 132 to ↑ 197)
Sofosbuvir/ Velpatasvir [Study conducted with COMPLERA coadministered with EPCLUSA; coadministration with EPCLUSA also results in comparable increases in tenofovir exposures when TDF is administered as ATRIPLA, STRIBILD® (elvitegravir/cobicistat/FTC/TDF), TRUVADA + atazanavir/ritonavir, or TRUVADA + darunavir/ritonavir.] | 400/100 once daily | 24 | ↑ 44; (↑ 33 to ↑ 55) | ↑ 40; (↑ 34 to ↑ 46) | ↑ 84; (↑ 76 to ↑ 92)
Sofosbuvir/ Velpatasvir [Administered as raltegravir + FTC/TDF.] | 400/100 once daily | 30 | ↑ 46; (↑ 39 to ↑ 54) | ↑ 40; (↑ 34 to ↑ 45) | ↑ 70; (↑ 61 to ↑ 79)
Sofosbuvir/ Velpatasvir/ Voxilaprevir [Comparison based on exposures when administered as darunavir + ritonavir + FTC/TDF.] | 400/100/100 + Voxilaprevir [Study conducted with additional voxilaprevir 100 mg to achieve voxilaprevir exposures expected in HCV-infected patients.] 100 once daily | 29 | ↑ 48; (↑ 36 to ↑ 61) | ↑ 39; (↑ 32 to ↑ 46) | ↑ 47; (↑ 38 to ↑ 56)
Sofosbuvir [Study conducted with efavirenz/emtricitabine/tenofovir disoproxil fumarate coadministered with sofosbuvir.] | 400 single dose | 16 | ↑ 25; (↑ 8 to ↑ 45) | ↔ | ↔
Tacrolimus | 0.05 mg/kg twice daily x 7 days | 21 | ↑ 13; (↑ 1 to ↑ 27) | ↔ | ↔

12.4 Microbiology

Mechanism of Action

Efavirenz

EFV is an NNRTI of HIV-1. EFV activity is mediated predominantly by noncompetitive inhibition of HIV-1 reverse transcriptase (RT). HIV-2 RT and human cellular DNA polymerases α, β, γ, and δ are not inhibited by EFV.

Lamivudine

3TC is a synthetic nucleoside analogue with activity against HIV-1 and HBV. Intracellularly, 3TC is phosphorylated to its active 5’‑triphosphate metabolite, lamivudine triphosphate (3TC-TP). The principal mode of action of 3TC‑TP is inhibition of HIV-1 reverse transcriptase (RT) via DNA chain termination after incorporation of the nucleotide analogue.

Tenofovir Disoproxil Fumarate

TDF is an acyclic nucleoside phosphonate diester analog of adenosine monophosphate. TDF requires initial diester hydrolysis for conversion to tenofovir and subsequent phosphorylations by cellular enzymes to form tenofovir diphosphate (TDF-DP), an obligate chain terminator. Tenofovir diphosphate inhibits the activity of HIV-1 reverse transcriptase (RT) and HBV RT by competing with the natural substrate deoxyadenosine 5’-triphosphate and, after incorporation into DNA, by DNA chain termination. Tenofovir diphosphate is a weak inhibitor of mammalian DNA polymerases α, β, and mitochondrial DNA polymerase γ.

Antiviral Activity

Efavirenz

The concentration of EFV inhibiting replication of wild-type laboratory adapted strains and clinical isolates in cell culture by 90 to 95% (EC90 to 95) ranged from 1.7 to 25 nM in lymphoblastoid cell lines, peripheral blood mononuclear cells (PBMCs), and macrophage/monocyte cultures. EFV demonstrated antiviral activity against clade B and most non-clade B isolates (subtypes A, AE, AG, C, D, F, G, J, N), but had reduced antiviral activity against group O viruses.

Lamivudine

The antiviral activity of 3TC against HIV-1 was assessed in a number of cell lines (including monocytes and fresh human peripheral blood lymphocytes (PBMCs) using standard susceptibility assays. EC50 values were in the range of 3 to 15,000 nM. (1 μM = 0.23 mcg/mL). The median EC50 values of 3TC were 60 nM (range: 20 to 70 nM), 35 nM (range: 30 to 40 nM), 30 nM (range: 20 to 90 nM), 20 nM (range: 3 to 40 nM), 30 nM (range: 1 to 60 nM), 30 nM (range: 20 to 70 nM), 30 nM (range: 3 to 70 nM), and 30 nM (range: 20 to 90 nM) against HIV-1 clades A-G and group O viruses (n = 3 except n = 2 for clade B), respectively. The EC50 values against HIV-2 isolates (n = 4) ranged from 3 to 120 nM in PBMCs. 3TC was not antagonistic to all tested anti-HIV agents. Ribavirin (50 μM) used in the treatment of chronic HCV infection decreased the anti-HIV-1 activity of 3TC by 3.5-fold in MT-4 cells.

Tenofovir Disoproxil Fumarate

The antiviral activity of tenofovir against laboratory and clinical isolates of HIV-1 was assessed in lymphoblastoid cell lines, primary monocyte/macrophage cells and peripheral blood lymphocytes. The EC50 (50% effective concentration) values for tenofovir were in the range of 0.04 μM to 8.5 μM. Tenofovir displayed antiviral activity in cell culture against HIV-1 clades A, B, C, D, E, F, G, and O (EC50 values ranged from 0.5 μM to 2.2 μM) and strain-specific activity against HIV-2 (EC50 values ranged from 1.6 μM to 5.5 μM). Please see the full prescribing information for VIREAD® for information regarding the inhibitory activity of TDF against HBV.

Resistance

Efavirenz

In cell culture, HIV-1 isolates with reduced susceptibility to EFV (> 380-fold increase in EC90 value) emerged rapidly in the presence of drug. Genotypic characterization of these viruses identified single amino acid substitutions L100I or V179D, double substitutions L100I/V108I, and triple substitutions L100I/V179D/Y181C in reverse transcriptase.

Clinical isolates with reduced susceptibility in cell culture to EFV have been obtained. One or more RT substitutions at amino acid positions A98, L100, K101, K103, V106, V108, Y188, G190, P225, F227 and M230 were observed in patients failing treatment with EFV in combination with indinavir, or with 3TC plus zidovudine. The K103N substitution was the most frequently observed.

Lamivudine

3TC-resistant variants of HIV‑1 have been selected in cell culture. Genotypic analysis showed that resistance was predominantly due to a methionine to valine or isoleucine (M184V/I) substitution in reverse transcriptase.

Tenofovir Disoproxil Fumarate

HIV-1 isolates with reduced susceptibility to tenofovir have been selected in cell culture. These viruses expressed a K65R substitution in RT and showed a 2- to 4-fold reduction in susceptibility to tenofovir. In addition, a K70E substitution in HIV-1 RT has been selected by tenofovir and results in low-level reduced susceptibility to tenofovir. K65R substitutions developed in some subjects failing a tenofovir disoproxil fumarate regimen.

Cross-Resistance

Efavirenz

Cross-resistance among NNRTIs has been observed. Clinical isolates previously characterized as EFV-resistant were also phenotypically resistant in cell culture to delavirdine and nevirapine compared to baseline. Delavirdine- and/or nevirapine-resistant clinical viral isolates with NNRTI resistance-associated substitutions (A98G, L100I, K101E/P, K103N/S, V106A, Y181X, Y188X, G190X, P225H, F227L, or M230L) showed reduced susceptibility to EFV in cell culture. Greater than 90% of NRTI-resistant clinical isolates tested in cell culture retained susceptibility to EFV.

Lamivudine

Cross-resistance among NRTIs has been observed. 3TC-resistant HIV-1 isolates were cross-resistant in cell culture to didanosine (ddI). Cross-resistance is also expected with abacavir and emtricitabine as these select M184V substitutions.

Tenofovir Disoproxil Fumarate

Cross-resistance among certain HIV-1 NRTIs has been observed. The K65R and K70E substitutions selected by tenofovir are also selected in some HIV-1-infected subjects treated with abacavir or didanosine. HIV-1 isolates with the K65R substitution also showed reduced susceptibility to FTC and 3TC. HIV-1 isolates from subjects (N = 20) whose HIV-1 expressed a mean of 3 zidovudine-associated RT amino acid substitutions (M41L, D67N, K70R, L210W, T215Y/F, or K219Q/E/N) showed a 3.1-fold decrease in the susceptibility to tenofovir. Subjects whose virus expressed an L74V substitution without zidovudine resistance-associated substitutions (N = 8) had reduced response to VIREAD. Limited data are available for patients whose virus expressed a Y115F substitution (N = 3), Q151M substitution (N = 2), or T69 insertion (N = 4), all of whom had a reduced response.

13 NONCLINICAL TOXICOLOGY

13.1 Carcinogenesis, Mutagenesis, Impairment of Fertility

Efavirenz

Long-term carcinogenicity studies in mice and rats were carried out with efavirenz. Mice were dosed with 0, 25, 75, 150, or 300 mg/kg/day for 2 years. Incidences of hepatocellular adenomas and carcinomas and pulmonary alveolar/bronchiolar adenomas were increased above background in females. No increases in tumor incidence above background were seen in males. There was no NOAEL in female established for this study because tumor findings occurred at all doses. AUC at the NOAEL (150 mg/kg) in the males was approximately 0.9 times that in humans at the recommended clinical dose. In the rat study, no increases in tumor incidence were observed at doses up to 100 mg/kg/day, for which AUCs were 0.1 (males) or 0.2 (females) times those in humans at the recommended clinical dose.

EFV tested negative in a battery of in vitro and in vivo genotoxicity assays. These included bacterial mutation assays in S. typhimurium and E. coli, mammalian mutation assays in Chinese hamster ovary cells, chromosome aberration assays in human peripheral blood lymphocytes or Chinese hamster ovary cells, and an in vivo mouse bone marrow micronucleus assay.

EFV did not impair mating or fertility of male or female rats, and did not affect sperm of treated male rats. The reproductive performance of offspring born to female rats given EFV was not affected. The AUCs at the NOAEL values in male (200 mg/kg) and female (100 mg/kg) rats were approximately ≤ 0.15 times that in humans at the recommended clinical dose.

Lamivudine

Long-term carcinogenicity studies with 3TC in mice and rats showed no evidence of carcinogenic potential at exposures up to 10 times (mice) and 58 times (rats) the human exposures at the recommended dose of 300 mg. 3TC was not mutagenic in a microbial mutagenicity assay, in an in vitro cell transformation assay, in a rat micronucleus test, in a rat bone marrow cytogenetic assay, and in assay for unscheduled DNA synthesis in rat liver. 3TC showed no evidence of in vivo genotoxic activity in the rat at oral doses of up to 2000 mg per kg, producing plasma levels of 35 to 45 times those in humans at the recommended dose for HIV‑1 infection. In a study of reproductive performance, 3TC administered to rats at doses up to 4000 mg per kg per day, producing plasma levels 47 to 70 times those in humans, revealed no evidence of impaired fertility and no effect on the survival, growth, and development to weaning of the offspring.

Tenofovir Disoproxil Fumarate

Long-term oral carcinogenicity studies of TDF in mice and rats were carried out at exposures up to approximately 16 times (mice) and 5 times (rats) those observed in humans at the therapeutic dose for HIV-1 infection. At the high dose in female mice, liver adenomas were increased at exposures 16 times that in humans. In rats, the study was negative for carcinogenic findings at exposures up to 5 times that observed in humans at the therapeutic dose.

TDF was mutagenic in the in vitro mouse lymphoma assay and negative in an in vitro bacterial mutagenicity test (Ames test). In an in vivo mouse micronucleus assay, TDF was negative when administered to male mice.

There were no effects on fertility, mating performance or early embryonic development when TDF was administered to male rats at a dose equivalent to 10 times the human dose based on body surface area comparisons for 28 days prior to mating and to female rats for 15 days prior to mating through day seven of gestation. There was, however, an alteration of the estrous cycle in female rats.

13.2 Animal Toxicology and/or Pharmacology

Efavirenz

Nonsustained convulsions were observed in 6 of 20 monkeys receiving EFV at doses yielding plasma AUC values 4- to 13-fold greater than those in humans given the recommended dose [see Warnings and Precautions (5.11)].

Tenofovir Disoproxil Fumarate

Tenofovir and TDF administered in toxicology studies to rats, dogs, and monkeys at exposures (based on AUCs) greater than or equal to 6-fold those observed in humans caused bone toxicity. In monkeys the bone toxicity was diagnosed as osteomalacia. Osteomalacia observed in monkeys appeared to be reversible upon dose reduction or discontinuation of tenofovir. In rats and dogs, the bone toxicity manifested as reduced bone mineral density. The mechanism(s) underlying bone toxicity is unknown.

Evidence of renal toxicity was noted in 4 animal species. Increases in serum creatinine, BUN, glycosuria, proteinuria, phosphaturia, and/or calciuria and decreases in serum phosphate were observed to varying degrees in these animals. These toxicities were noted at exposures (based on AUCs) 2 to 20 times higher than those observed in humans. The relationship of the renal abnormalities, particularly the phosphaturia, to the bone toxicity is not known.

14 CLINICAL STUDIES

14.1 Clinical Efficacy in Patients with HIV-1 Infection

Treatment-Naïve Adult Patients

The efficacy of EFV 600 mg, 3TC 300 mg, and TDF 300 mg in the treatment of HIV-1 infection in adults with no antiretroviral treatment history was established in Trial 903.

Trial 903

Data through 144 weeks are reported for Trial 903, a double-blind, active-controlled multicenter trial comparing EFV 600 mg + 3TC 300 mg + TDF 300 mg vs. EFV 600 mg + 3TC 300 mg + stavudine (d4T) 40 mg in 600 antiretroviral-naïve subjects. Subjects had a mean age of 36 years (range 18-64); 74% were male, 64% were Caucasian, and 20% were Black. The mean baseline CD4+ cell count was 279 cells/mm3 (range 3-956) and median baseline plasma HIV-1 RNA was 77,600 copies/mL (range 417−5,130,000). Subjects were stratified by baseline HIV-1 RNA and CD4+ cell count. Forty-three percent of subjects had baseline viral loads > 100,000 copies/mL and 39% had CD4+ cell counts < 200 cells/mm3. Table 9 provides treatment outcomes through 48 and 144 weeks.

Table 9. Outcomes of Randomized Treatment at Week 48 and 144 (Study 903)
Outcomes | At Week 48 |  | At Week 144
Outcomes | EFV + 3TC + TDF; (N = 299) | EFV + 3TC + d4T; (N = 301) | EFV + 3TC + TDF; (N = 299) | EFV + 3TC + d4T; (N = 301)
Responder [Subjects achieved and maintained confirmed HIV-1 RNA < 400 copies/mL through Week 48 and 144.] | 79% | 82% | 68% | 62%
Virologic failure [Includes confirmed viral rebound and failure to achieve confirmed < 400 copies/mL through Week 48 and 144.] | 6% | 4% | 10% | 8%
Rebound | 5% | 3% | 8% | 7%
Never suppressed | 0% | 1% | 0% | 0%
Added an antiretroviral agent | 1% | 1% | 2% | 1%
Death | < 1% | 1% | < 1% | 2%
Discontinued due to adverse event | 6% | 6% | 8% | 13%
Discontinued for other reasons [Includes lost to follow-up, subject’s withdrawal, noncompliance, protocol violation and other reasons.] | 8% | 7% | 14% | 15%

Achievement of plasma HIV-1 RNA concentrations of < 400 copies/mL at Week 144 was similar between the two treatment groups for the population stratified at baseline on the basis of HIV-1 RNA concentration (> or ≤ 100,000 copies/mL) and CD4+ cell count (< or ≥ 200 cells/mm3). Through 144 weeks of therapy, 62% and 58% of subjects in the TDF and d4T arms, respectively, achieved and maintained confirmed HIV-1 RNA < 50 copies/mL. The mean increase from baseline in CD4+ cell count was 263 cells/mm3 for the TDF arm and 283 cells/mm3 for the d4T arm.

Through 144 weeks, 11 subjects in the TDF group and 9 subjects in the d4T group experienced a new CDC Class C event.

16 HOW SUPPLIED/STORAGE AND HANDLING

SYMFI (efavirenz, lamivudine and tenofovir disoproxil fumarate) Tablets 600 mg/300 mg/300 mg are white, film-coated, capsule shaped, debossed with M 152 on one side of the tablet and plain on the other side. They are available as follows:

NDC 49502-475-93
cartons containing bottles of 30 tablets with desiccant, induction seal and child-resistant cap

NDC 49502-475-77
cartons containing bottles of 90 tablets with desiccant, induction seal and child-resistant cap

Store below 30°C (86°F).

Keep the bottle tightly closed.

Dispense in original container.

Do not use if seal over bottle opening is broken or missing.

17 PATIENT COUNSELING INFORMATION

Advise the patient to read the FDA-approved patient labeling (Patient Information).

Drug Interactions: SYMFI may interact with many drugs; therefore, advise patients to report to their healthcare provider the use of any other prescription, nonprescription medication, or herbal products, particularly St. John’s wort [see Contraindications (4) and Drug Interactions (7)].

Post Treatment Acute Exacerbation of Hepatitis B in Patients with HBV Co-Infection: Inform patients that severe acute exacerbations of hepatitis have been reported in patients who are infected with HBV or coinfected with HBV and HIV-1 and have discontinued 3TC and TDF, components of SYMFI. Test patients with HIV-1 for hepatitis B virus (HBV) before initiating antiretroviral therapy. In patients with chronic hepatitis B, it is important to obtain HIV antibody testing prior to initiating 3TC and TDF, components of SYMFI [see Warnings and Precautions (5.1)].

Lactic Acidosis and Severe Hepatomegaly: Inform patients that lactic acidosis and severe hepatomegaly with steatosis, including fatal cases, have been reported. Treatment with SYMFI should be suspended in any patient who develops clinical symptoms suggestive of lactic acidosis or pronounced hepatotoxicity (including nausea, vomiting, unusual or unexpected stomach discomfort, and weakness) [see Warnings and Precautions (5.2)].

New Onset or Worsening Renal Impairment: Inform patients that renal impairment, including cases of acute renal failure and Fanconi syndrome, has been reported. Advise patients with impaired renal function (i.e., creatinine clearance less than 50 mL/min) or patients with end-stage renal disease (ESRD) requiring hemodialysis to avoid SYMFI with concurrent or recent use of a nephrotoxic agent (e.g., high-dose or multiple NSAIDs) for patients [see Dosage and Administration (2.3), Warnings and Precautions (5.4)].

Psychiatric Symptoms: Inform patients that serious psychiatric symptoms including severe depression, suicide attempts, aggressive behavior, delusions, paranoia, psychosis-like symptoms and catatonia have been reported in patients receiving EFV [see Warnings and Precautions (5.5)]. Advise patients to seek immediate medical evaluation if they experience severe psychiatric adverse experiences. Advise patients to inform their physician of any history of mental illness or substance abuse.

Nervous System Symptoms: Inform patients that central nervous system symptoms (NSS) including dizziness, insomnia, impaired concentration, drowsiness, and abnormal dreams are commonly reported during the first weeks of therapy with EFV, a component of SYMFI [see Warnings and Precautions (5.6)]. Dosing at bedtime may improve the tolerability of these symptoms, which are likely to improve with continued therapy. Alert patients to the potential for additive effects when used concomitantly with alcohol or psychoactive drugs. Instruct patients that if they experience NSS they should avoid potentially hazardous tasks such as driving or operating machinery.

Inform patients that there is a risk of developing late-onset neurotoxicity, including ataxia and encephalopathy, which may occur months to years after beginning efavirenz therapy [see Warnings and Precautions (5.6)].

Embryo-Fetal Toxicity: Advise female patients that EFV, a component of SYMFI may cause fetal harm when administered during the first trimester to a pregnant woman. Advise females of reproductive potential to use effective contraception as well as a barrier method during treatment with SYMFI and for 12 weeks after discontinuation of use. Advise patients to contact their healthcare provider if they plan to become pregnant, become pregnant, or if pregnancy is suspected during treatment with SYMFI [see Warnings and Precautions (5.7), Use in Specific Populations (8.1, 8.3)].

Rash: Inform patients that rash is a common side effect of EFV [see Warnings and Precautions (5.8)]. Rashes usually go away without any change in treatment. However, since rash may be serious, patients should be advised to contact their physician promptly if rash occurs.

Hepatotoxicity: Inform patients to watch for early warning signs of liver inflammation or failure, such as fatigue, weakness, lack of appetite, nausea and vomiting, as well as later signs such as jaundice, confusion, abdominal swelling, and discolored feces and to consult their healthcare provider promptly if such symptoms occur [see Warnings and Precautions (5.9)].

Pancreatitis: Advise patients or guardians to monitor pediatric patients for signs and symptoms of pancreatitis [see Warnings and Precautions (5.10)].

Convulsions: Advise patients that convulsions have been observed in patients receiving EFV, a component of SYMFI, generally in patients with known medical history of seizures [see Warnings and Precautions (5.11)].

Lipid Elevations: Advise patients treatment with EFV, a component of SYMFI has resulted in increases in the concentration of total cholesterol and triglycerides [see Warnings and Precautions (5.12)].

Bone Loss and Mineralization Effects: Inform patients that decreases in bone mineral density have been observed with the use of 3TC and TDF, components of SYMFI, in patients with HIV [see Warnings and Precautions (5.13)].

Immune Reconstitution Syndrome: Advise patients to inform their healthcare provider immediately of any symptoms of infection, as in some patients with advanced HIV infection, signs and symptoms of inflammation from previous infections may occur soon after anti-HIV treatment is started [see Warnings and Precautions (5.14)].

Fat Redistribution: Inform patients that redistribution or accumulation of body fat may occur in patients receiving antiretroviral therapy, including SYMFI, and that the cause and long‑term health effects of these conditions are not known at this time [see Warnings and Precautions (5.15)].

Administration Instructions: Inform patients that it is important to take SYMFI once daily on a regular dosing schedule on an empty stomach, preferably at bedtime, and to avoid missing doses as it can result in development of resistance. Advise patients if a dose is missed, take it as soon as possible unless it is almost time for the next dose. Also advise patients that dosing at bedtime may improve the tolerability of nervous system symptoms [see Dosage and Administration (2.2)].

Pregnancy Registry: Advise patients that there is an antiretroviral pregnancy registry to monitor fetal outcomes in women exposed to SYMFI [see Use in Specific Populations (8.1)].

Lactation: Instruct women with HIV-1 infection not to breastfeed because HIV-1 can be passed to the baby in breast milk [see Use in Specific Populations (8.2)].

SYMFI® is a registered trademark of Mylan Pharmaceuticals Inc.

Other brands listed are the registered trademarks of their respective owners and are not trademarks of Mylan Laboratories Limited or Mylan Pharmaceuticals Inc.

Rx only

Manufactured for:
Mylan Specialty L.P.
Morgantown, WV 26505 U.S.A.

Manufactured by:
Mylan Laboratories Limited
Hyderabad — 500 096, India

Patient Information

SYMFI® (SIM-fee)
(efavirenz, lamivudine and tenofovir disoproxil fumarate)
tablets

What is the most important information I should know about SYMFI?

SYMFI can cause serious side effects, including:

- Worsening of Hepatitis B virus infection. If you have Human Immunodeficiency Virus type 1 (HIV-1) and Hepatitis B Virus (HBV) infection, your HBV may get worse (flare-up) if you stop taking SYMFI. A “flare-up” is when your HBV infection suddenly returns in a worse way than before. Your healthcare provider will test you for HBV infection before you start treatment with SYMFI.
  - It is not known if SYMFI is safe and effective in people who have both HIV-1 and HBV infection.
  - Do not run out of SYMFI. Refill your prescription or talk to your healthcare provider before your SYMFI is all gone.
  - Do not stop SYMFI without first talking to your healthcare provider. If you stop taking SYMFI, your healthcare provider will need to check your health often and do blood tests regularly for several months to check your liver.

For more information about side effects, see “What are the possible side effects of SYMFI?”

What is SYMFI?

SYMFI is a prescription medicine that is used without other antiretroviral medicines to treat Human Immunodeficiency Virus-1 (HIV-1) in adults and children weighing at least 88 pounds (40 kg).

HIV-1 is the virus that causes AIDS (Acquired Immune Deficiency Syndrome).

SYMFI contains the prescription medicines efavirenz, lamivudine and tenofovir disoproxil fumarate.

Do not take SYMFI if you:

- are allergic to efavirenz, lamivudine, tenofovir disoproxil fumarate, or any of the ingredients in SYMFI. See the end of this Patient Information leaflet for a complete list of ingredients in SYMFI.
- are currently taking elbasvir and grazoprevir.

Before you take SYMFI, tell your healthcare provider about all of your medical conditions, including if you:

- have liver problems, including hepatitis B or C infection
- have kidney problems, including end-stage renal disease (ESRD) that requires dialysis
- have a history of mental health problems
- have a history of drug or alcohol abuse
- have a heart problem, including QT prolongation
- have bone problems, including a history of bone fractures
- have a history of seizures
- are pregnant or plan to become pregnant. SYMFI may harm your unborn baby.
  - You should not become pregnant during treatment with SYMFI. Tell your healthcare provider right away if you think you may be pregnant or become pregnant during treatment with SYMFI.
  - Females who are able to become pregnant should use effective birth control during treatment with SYMFI and for 12 weeks after stopping treatment. A barrier form of birth control should always be used along with another type of birth control.
  - If you are able to become pregnant, your healthcare provider should do a pregnancy test before you start SYMFI.
Pregnancy Registry. There is a pregnancy registry for women who take SYMFI during pregnancy. The purpose of this registry is to collect information about the health of you and your baby. Talk to your healthcare provider about how you can take part in this registry.
- are breastfeeding or plan to breastfeed. Do not breastfeed if you take SYMFI.
  - You should not breastfeed if you have HIV-1 because of the risk of passing HIV-1 to your baby.
  - Talk to your healthcare provider about the best way to feed your baby.

Tell your healthcare provider about all the medicines you take, including prescription and over-the-counter medicines, vitamins and herbal supplements.

Some medicines interact with SYMFI. SYMFI may affect the way other medicines work, and other medicines may affect how SYMFI works. Keep a list of your medicines and show it to your healthcare provider and pharmacist when you get a new medicine.

- You can ask your healthcare provider or pharmacist for a list of medicines that interact with SYMFI.
- Do not start taking a new medicine without telling your healthcare provider. Your healthcare provider can tell you if it is safe to take SYMFI with other medicines.

How should I take SYMFI?

- Take SYMFI exactly as your healthcare provider tells you to take it.
- Take SYMFI 1 time each day, preferably at bedtime. Taking SYMFI at bedtime might help to make some of the side effects less bothersome.
- Take SYMFI on an empty stomach.
- Do not miss a dose of SYMFI. If you miss a dose, take the missed dose as soon as you remember. If it is almost time for your next dose of SYMFI, do not take the missed dose. Take the next dose at your regular time.
- Stay under the care of your healthcare provider during treatment with SYMFI.
- Do not run out of SYMFI. The virus in your blood may increase and the virus may become harder to treat. When your supply starts to run low, get more from your healthcare provider or pharmacy.
- If you take too much SYMFI, go to the nearest hospital emergency room right away.

What should I avoid while taking SYMFI?

You should avoid taking medicines that contain sorbitol during treatment with SYMFI.

What are the possible side effects of SYMFI?

SYMFI may cause serious side effects, including:

- See “What is the most important information I should know about SYMFI?”
- Build-up of an acid in your blood (lactic acidosis). Lactic acidosis can happen in some people who take SYMFI. Lactic acidosis is a serious medical emergency that can lead to death. Call your healthcare provider right away if you get any of the following symptoms that could be signs of lactic acidosis:

- feel very weak or tired
- unusual (not normal) muscle pain
- trouble breathing
- stomach pain with nausea or vomiting

- feel cold, especially in your arms and legs
- feel dizzy or lightheaded
- have a fast or irregular heartbeat

- Severe liver problems can happen in people who take SYMFI. In some cases, these severe liver problems can lead to death. Your liver may become large (hepatomegaly) and you may develop fat in your liver (steatosis). Inflammation of your liver (hepatitis) that can lead to liver failure requiring a liver transplant has been reported in some people treated with SYMFI. Your healthcare provider may do blood tests to check your liver before and during treatment with SYMFI.
  Call your healthcare provider right away if you get any of the following signs or symptoms of liver problems:

- your skin or the white part of your eyes turns yellow (jaundice)
- dark or “tea-colored” urine
- light-colored stools (bowel movements)
- confusion
- tiredness

- loss of appetite for several days or longer
- nausea and vomiting
- pain, aching, or tenderness on the right side of your stomach-area
- weakness
- stomach (abdomen) swelling

You may be more likely to get lactic acidosis or serious liver problems if you are female or very overweight (obese).
2. New or worse kidney problems, including kidney failure. Your healthcare provider may do blood and urine tests to check your kidneys before and during treatment with SYMFI. Tell your healthcare provider if you get signs and symptoms of kidney problems, including bone pain that does not go away or worsening bone pain, pain in your arms, hands, legs or feet, broken (fractured) bones, muscle pain or weakness.
3. Serious mental health problems. Get medical help right away if you get any of the following symptoms:
4. feel sad or hopeless
5. feel anxious or restless
6. do not trust other people
7. hear or see things that are not real
8. are not able to move or speak normally
9. have thoughts of hurting yourself (suicide) or have tried to hurt yourself or others
10. are not able to tell the difference between what is true or real and what is false or unreal
11. Nervous system symptoms are common in people who take SYMFI and can be severe. These symptoms usually begin during the first or second day of treatment with SYMFI and usually go away after 2 to 4 weeks of treatment. Some symptoms may occur months to years after beginning SYMFI therapy. These symptoms may become worse if you drink alcohol, take a medicine for mental health problems, or use certain street drugs during treatment with SYMFI. Symptoms may include:

- dizziness
- trouble sleeping
- unusual dreams

- trouble concentrating
- drowsiness
- lack of coordination or balance

If you have dizziness, trouble concentrating or drowsiness, do not drive a car, use machinery, or do anything that needs you to be alert.
Some nervous system symptoms (e.g., confusion, slow thoughts and physical movement, and delusions [false beliefs] or hallucinations [seeing or hearing things that others do not see or hear]) may occur months to years after beginning SYMFI therapy. Promptly contact your health care provider should any of these symptoms occur.
4. Skin reactions and allergic reactions. Skin reactions or rash can happen and can sometimes be severe. Skin rash usually goes away without any change in treatment. If you develop a rash or a rash with any of the following symptoms, call your healthcare provider right away:

- itching
- fever
- swelling of your face
- blisters or skin lesions

- peeling skin
- mouth sores
- red or inflamed eyes

- Risk of inflammation of the pancreas (pancreatitis). Children may be at risk for developing pancreatitis during treatment with SYMFI if they:
  - have taken nucleoside analogue medicines in the past
  - have a history of pancreatitis
  - have other risk factors for pancreatitis
Call your healthcare provider right away if your child develops signs and symptoms of pancreatitis including severe upper stomach-area pain, with or without nausea and vomiting. Your healthcare provider may tell you to stop giving SYMFI to your child if their symptoms and blood test results show that your child may have pancreatitis.
- Seizures. Seizures are more likely to happen if you have had seizures in the past.
- Increases in blood fat levels (cholesterol and triglycerides). Your healthcare provider will check your blood fat levels before and during treatment with SYMFI.
- Bone problems can happen in some people who take SYMFI. Bone problems include bone pain, softening or thinning (which may lead to fractures). Your healthcare provider may need to do tests to check your bones. Tell your healthcare provider if you have any bone pain, pain in your hands or feet, or muscle pain or weakness during treatment with SYMFI.
- Changes in your immune system (Immune Reconstitution Syndrome) can happen when you start taking HIV-1 medicines. Your immune system may get stronger and begin to fight infections that have been hidden in your body for a long time. Tell your healthcare provider if you start having new symptoms after starting your HIV-1 medicine.
- Changes in body fat can happen in some people who take HIV-1 medicines. These changes may include increased amount of fat in the upper back and neck (“buffalo hump”), breast, and around the main part of your body (trunk). Loss of fat from the legs, arms, and face may also happen. The cause and long-term health effects of these conditions are not known.
- Changes in the electrical activity of your heart called QT prolongation. QT prolongation can cause irregular heartbeats that can be life-threatening. Tell your healthcare provider if you feel faint, lightheaded, dizzy, or feel your heart beating irregularly or fast during treatment with SYMFI.

The most common side effects of SYMFI are:

- trouble concentrating
- headache
- not feeling well
- nasal signs and symptoms
- rash
- trouble sleeping
- depression
- cough

- abnormal dreams
- nausea
- tiredness
- diarrhea
- dizziness
- pain
- weakness

Tell your healthcare provider if you have any side effect that bothers you or that does not go away.

These are not all the possible side effects of SYMFI. Call your doctor for medical advice about side effects. You may report side effects to FDA at 1-800-FDA-1088.

How should I store SYMFI?

- Store SYMFI tablets below 86°F (30°C).
- Keep SYMFI tablets in the original container.

Keep SYMFI and all medicines out of the reach of children.

General information about the safe and effective use of SYMFI.

Medicines are sometimes prescribed for purposes other than those listed in a Patient Information leaflet. Do not use SYMFI for a condition for which it was not prescribed. Do not give SYMFI to other people, even if they have the same symptoms that you have. It may harm them. If you would like more information, talk with your healthcare provider. You can ask your pharmacist or healthcare provider for information about SYMFI that is written for health professionals.

What are the ingredients in SYMFI?

Active ingredient: efavirenz, lamivudine, and tenofovir disoproxil fumarate

Inactive ingredients: croscarmellose sodium, hydroxypropyl cellulose, lactose monohydrate, magnesium stearate, microcrystalline cellulose, polyethylene glycol, polyvinyl alcohol, sodium chloride, sodium lauryl sulfate, talc and titanium dioxide.

SYMFI® is a registered trademark of Mylan Pharmaceuticals Inc.

Other brands listed are the registered trademarks of their respective owners and are not trademarks of Mylan Laboratories Limited or Mylan Pharmaceuticals Inc.

Manufactured for:
Mylan Specialty L.P.
Morgantown, WV 26505 U.S.A.

Manufactured by:
Mylan Laboratories Limited
Hyderabad — 500 096, India

75075345
MS:TLET:R2

For more information, call Mylan at 1-877-446-3679 (1-877-4-INFO-RX).

This Patient Information has been approved by the U.S. Food and Drug Administration. Revised: 10/2019

PRINCIPAL DISPLAY PANEL - 600 mg/300 mg/300 mg

NDC 49502-475-93 Rx only

SYMFI®
(efavirenz, lamivudine,
and tenofovir disoproxil
fumarate) tablets
600 mg/300 mg/300 mg*

Note to pharmacist: Do not cover
ALERT box with pharmacy label.

ALERT: Find out about
medicines that should NOT
be taken with SYMFI®.

30 tablets

*Each film-coated tablet contains:
Efavirenz, USP 600 mg
Lamivudine, USP 300 mg
Tenofovir Disoproxil Fumarate 300 mg
(equivalent to 245 mg of tenofovir
disoproxil)

Usual Dosage: See accompanying
prescribing information.

Keep this and all medication
out of the reach of children.

Store below 30°C (86°F).

Dispense only in original container.
Keep container tightly closed.

Manufactured for:
Mylan Specialty L.P.
Morgantown, WV 26505 U.S.A.

Made in India

Code No.: MP/DRUGS/25/1/2014

MS:MXI:47593:1C:R3

Mylan.com

SYMFI® is a registered
trademark of Mylan
Pharmaceuticals Inc.